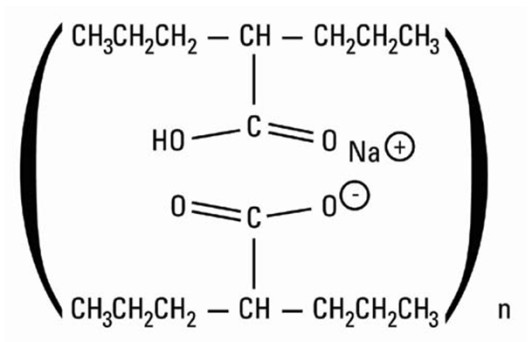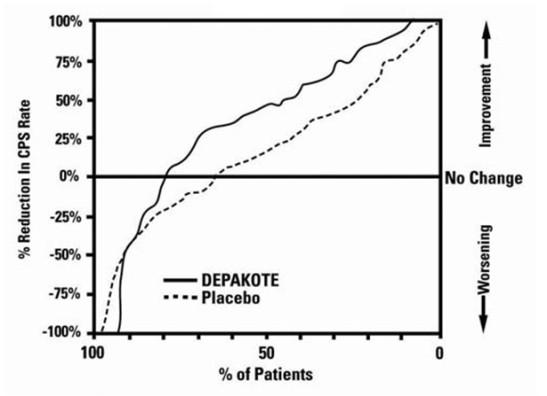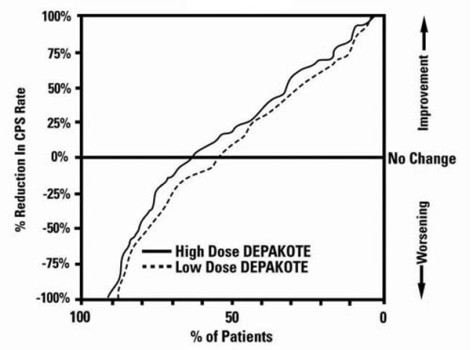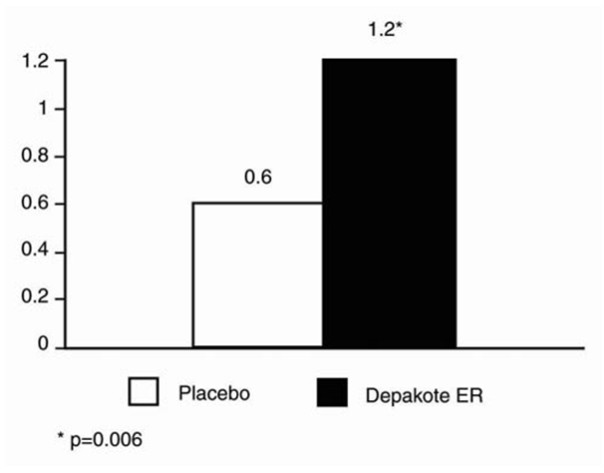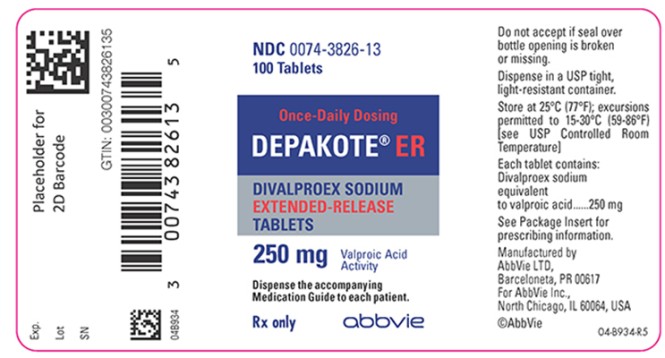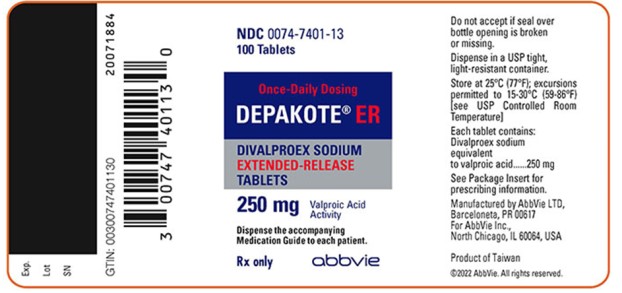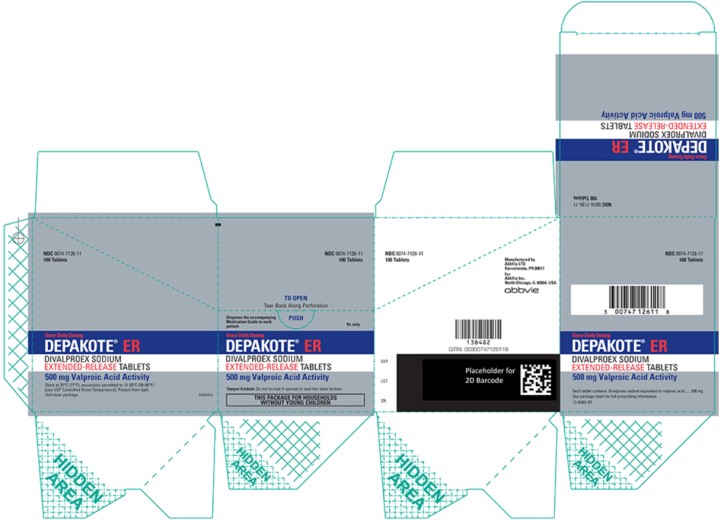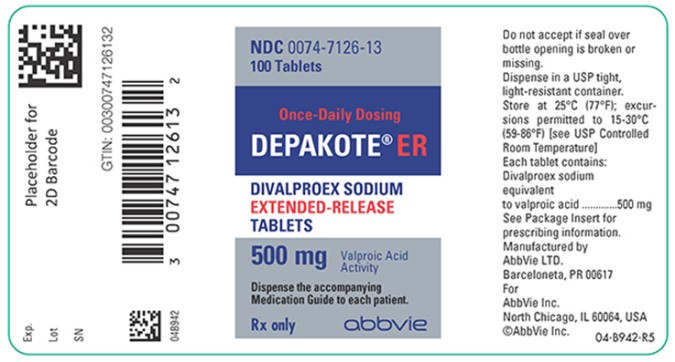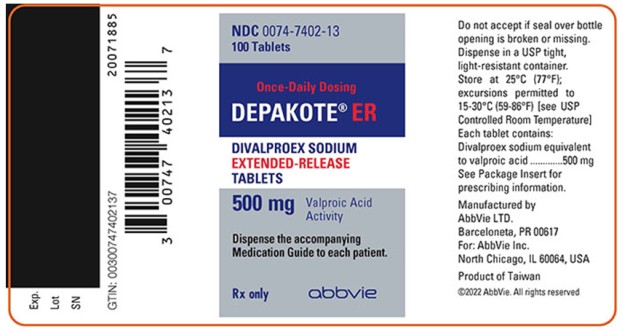 DRUG LABEL: Depakote
NDC: 0074-3826 | Form: TABLET, EXTENDED RELEASE
Manufacturer: AbbVie Inc.
Category: prescription | Type: HUMAN PRESCRIPTION DRUG LABEL
Date: 20250501

ACTIVE INGREDIENTS: DIVALPROEX SODIUM 250 mg/1 1
INACTIVE INGREDIENTS: TITANIUM DIOXIDE; SILICON DIOXIDE; POTASSIUM SORBATE; PROPYLENE GLYCOL; FD&C BLUE NO. 1; CELLULOSE, MICROCRYSTALLINE; TRIACETIN; LACTOSE, UNSPECIFIED FORM; HYPROMELLOSE, UNSPECIFIED; POLYETHYLENE GLYCOL, UNSPECIFIED

HIGHLIGHTS OF PRESCRIBING INFORMATION

These highlights do not include all the information needed to use Depakote ER safely and effectively. See full prescribing information for Depakote ER.
Depakote ER (divalproex sodium) extended-release tablets, for oral use
Initial U.S. Approval: 2000

RECENT MAJOR CHANGES

Contraindications (4) | 5/2025
Warnings and Precautions (5.13, 5.14) | 5/2025

WARNING: LIFE THREATENING ADVERSE REACTIONS

See full prescribing information for complete boxed warning.

- Hepatotoxicity, including fatalities, usually during the first 6 months of treatment. Children under the age of two years and patients with mitochondrial disorders are at higher risk. Monitor patients closely, and perform serum liver testing prior to therapy and at frequent intervals thereafter (5.1)
- Fetal Risk, particularly neural tube defects, other major malformations, and decreased IQ (5.2, 5.3, 5.4)
- Pancreatitis, including fatal hemorrhagic cases (5.5)

1 INDICATIONS AND USAGE

Depakote ER is indicated for:

- Acute treatment of manic or mixed episodes associated with bipolar disorder, with or without psychotic features (1.1)
- Monotherapy and adjunctive therapy of complex partial seizures and simple and complex absence seizures; adjunctive therapy in patients with multiple seizure types that include absence seizures (1.2)
- Prophylaxis of migraine headaches (1.3)

2 DOSAGE AND ADMINISTRATION

- Depakote ER is intended for once-a-day oral administration. Depakote ER should be swallowed whole and should not be crushed or chewed (2.1, 2.2).
- Mania: Initial dose is 25 mg/kg/day, increasing as rapidly as possible to achieve therapeutic response or desired plasma level (2.1). The maximum recommended dosage is 60 mg/kg/day (2.1, 2.2).
- Complex Partial Seizures: Start at 10 to 15 mg/kg/day, increasing at 1 week intervals by 5 to 10 mg/kg/day to achieve optimal clinical response; if response is not satisfactory, check valproate plasma level; see full prescribing information for conversion to monotherapy (2.2). The maximum recommended dosage is 60 mg/kg/day (2.1, 2.2).
- Absence Seizures: Start at 15 mg/kg/day, increasing at 1 week intervals by 5 to 10 mg/kg/day until seizure control or limiting side effects (2.2). The maximum recommended dosage is 60 mg/kg/day (2.1, 2.2).
- Migraine: The recommended starting dose is 500 mg/day for 1 week, thereafter increasing to 1,000 mg/day (2.3).

3 DOSAGE FORMS AND STRENGTHS

Tablets: 250 mg and 500 mg (3)

4 CONTRAINDICATIONS

- Hepatic disease or significant hepatic dysfunction (4, 5.1)
- Known mitochondrial disorders caused by mutations in mitochondrial DNA polymerase γ (POLG) (4, 5.1)
- Suspected POLG-related disorder in children under two years of age (4, 5.1)
- Known hypersensitivity to the drug (4, 5.12)
- Urea cycle disorders (4, 5.6)
- Prophylaxis of migraine headaches: Pregnant women, women of childbearing potential not using effective contraception (4, 8.1)

5 WARNINGS AND PRECAUTIONS

- Birth defects, decreased IQ, and neurodevelopmental disorders following in utero exposure: Should not be used to treat women with epilepsy or bipolar disorder who are pregnant or who plan to become pregnant or to treat a woman of childbearing potential unless other medications have failed to provide adequate symptom control or are otherwise unacceptable (5.2, 5.3, 5.4)
- Pancreatitis: Depakote ER should ordinarily be discontinued (5.5)
- Suicidal behavior or ideation: Antiepileptic drugs, including Depakote ER, increase the risk of suicidal thoughts or behavior (5.7)
- Bleeding and other hematopoietic disorders: Monitor platelet counts and coagulation tests (5.8)
- Hyperammonemia and hyperammonemic encephalopathy: Measure ammonia level if unexplained lethargy and vomiting or changes in mental status, and also with concomitant topiramate use; consider discontinuation of valproate therapy (5.6, 5.9, 5.10)
- Hypothermia: Hypothermia has been reported during valproate therapy with or without associated hyperammonemia. This adverse reaction can also occur in patients using concomitant topiramate (5.11)
- Drug Reaction with Eosinophilia and Systemic Symptoms (DRESS)/Multiorgan hypersensitivity reactions, serious dermatologic reactions, and angioedema: Discontinue Depakote ER unless an alternate etiology is established (5.12, 5.13, 5.14)

6 ADVERSE REACTIONS

- Most common adverse reactions (reported ≥15% for any indication) are abdominal pain, alopecia, asthenia, diarrhea, diplopia, dizziness, dyspepsia, headache, infection, insomnia, nausea, somnolence, thrombocytopenia, tremor, vomiting (6.1, 6.2, 6.3).
- The safety and tolerability of valproate in pediatric patients were shown to be comparable to those in adults (8.4).

To report SUSPECTED ADVERSE REACTIONS, contact AbbVie Inc. at 1-800-633-9110 or FDA at 1-800-FDA-1088 or www.fda.gov/medwatch.

7 DRUG INTERACTIONS

- Hepatic enzyme-inducing drugs (e.g., phenytoin, carbamazepine, phenobarbital, primidone, rifampin) can increase valproate clearance, while enzyme inhibitors (e.g., felbamate) can decrease valproate clearance. Therefore, increased monitoring of valproate and concomitant drug concentrations and dosage adjustment are indicated whenever enzyme-inducing or inhibiting drugs are introduced or withdrawn (7.1)
- Aspirin, carbapenem antibiotics, estrogen-containing hormonal contraceptives, methotrexate: Monitoring of valproate concentrations is recommended (7.1)
- Co-administration of valproate can affect the pharmacokinetics of other drugs (e.g., diazepam, ethosuximide, lamotrigine, phenytoin) by inhibiting their metabolism or protein binding displacement (7.2)
- Patients stabilized on rufinamide should begin valproate therapy at a low dose, and titrate to clinically effective dose (7.2)
- Dosage adjustment of amitriptyline/nortriptyline, propofol, warfarin, and zidovudine may be necessary if used concomitantly with Depakote ER (7.2)
- Topiramate: Hyperammonemia and encephalopathy (5.10, 7.3)
- Cannabidiol: ALT and/or AST elevation (7.4)

8 USE IN SPECIFIC POPULATIONS

- Pregnancy: Depakote ER can cause congenital malformations including neural tube defects, decreased IQ, and neurodevelopmental disorders (5.2, 5.3, 8.1)
- Geriatric: Reduce starting dose; increase dosage more slowly; monitor fluid and nutritional intake, and somnolence (5.16, 8.5)

FULL PRESCRIBING INFORMATION

WARNING: LIFE THREATENING ADVERSE REACTIONS

Hepatotoxicity

General Population: Hepatic failure resulting in fatalities has occurred in patients receiving valproate and its derivatives. These incidents usually have occurred during the first six months of treatment. Serious or fatal hepatotoxicity may be preceded by non-specific symptoms such as malaise, weakness, lethargy, facial edema, anorexia, and vomiting. In patients with epilepsy, a loss of seizure control may also occur. Patients should be monitored closely for appearance of these symptoms. Serum liver tests should be performed prior to therapy and at frequent intervals thereafter, especially during the first six months [see Warnings and Precautions (5.1)].

Children under the age of two years are at a considerably increased risk of developing fatal hepatotoxicity, especially those on multiple anticonvulsants, those with congenital metabolic disorders, those with severe seizure disorders accompanied by mental retardation, and those with organic brain disease. When Depakote ER is used in this patient group, it should be used with extreme caution and as a sole agent. The benefits of therapy should be weighed against the risks. The incidence of fatal hepatotoxicity decreases considerably in progressively older patient groups.

Patients with Mitochondrial Disease: There is an increased risk of valproate-induced acute liver failure and resultant deaths in patients with hereditary neurometabolic syndromes caused by DNA mutations of the mitochondrial DNA Polymerase γ (POLG) gene (e.g., Alpers Huttenlocher Syndrome). Depakote ER is contraindicated in patients known to have mitochondrial disorders caused by POLG mutations and children under two years of age who are clinically suspected of having a mitochondrial disorder [see Contraindications (4)]. In patients over two years of age who are clinically suspected of having a hereditary mitochondrial disease, Depakote ER should only be used after other anticonvulsants have failed. This older group of patients should be closely monitored during treatment with Depakote ER for the development of acute liver injury with regular clinical assessments and serum liver testing. POLG mutation screening should be performed in accordance with current clinical practice [see Warnings and Precautions (5.1)].

Fetal Risk

Valproate can cause major congenital malformations, particularly neural tube defects (e.g., spina bifida). In addition, valproate can cause decreased IQ scores and neurodevelopmental disorders following in utero exposure.

Valproate is therefore contraindicated for prophylaxis of migraine headaches in pregnant women and in women of childbearing potential who are not using effective contraception [see Contraindications (4)]. Valproate should not be used to treat women with epilepsy or bipolar disorder who are pregnant or who plan to become pregnant unless other medications have failed to provide adequate symptom control or are otherwise unacceptable.

Valproate should not be administered to a woman of childbearing potential unless other medications have failed to provide adequate symptom control or are otherwise unacceptable. In such situations, effective contraception should be used [see Warnings and Precautions (5.2, 5.3, 5.4)].

A Medication Guide describing the risks of valproate is available for patients [see Patient Counseling Information (17)].

Pancreatitis

Cases of life-threatening pancreatitis have been reported in both children and adults receiving valproate. Some of the cases have been described as hemorrhagic with a rapid progression from initial symptoms to death. Cases have been reported shortly after initial use as well as after several years of use. Patients and guardians should be warned that abdominal pain, nausea, vomiting, and/or anorexia can be symptoms of pancreatitis that require prompt medical evaluation. If pancreatitis is diagnosed, valproate should ordinarily be discontinued. Alternative treatment for the underlying medical condition should be initiated as clinically indicated [see Warnings and Precautions (5.5)].

1 INDICATIONS AND USAGE

1.1 Mania

Depakote ER is a valproate and is indicated for the treatment of acute manic or mixed episodes associated with bipolar disorder, with or without psychotic features. A manic episode is a distinct period of abnormally and persistently elevated, expansive, or irritable mood. Typical symptoms of mania include pressure of speech, motor hyperactivity, reduced need for sleep, flight of ideas, grandiosity, poor judgment, aggressiveness, and possible hostility. A mixed episode is characterized by the criteria for a manic episode in conjunction with those for a major depressive episode (depressed mood, loss of interest or pleasure in nearly all activities).

The efficacy of Depakote ER is based in part on studies of Depakote (divalproex sodium delayed release tablets) in this indication, and was confirmed in a 3-week trial with patients meeting DSM-IV TR criteria for bipolar I disorder, manic or mixed type, who were hospitalized for acute mania [see Clinical Studies (14.1)].

The effectiveness of valproate for long-term use in mania, i.e., more than 3 weeks, has not been demonstrated in controlled clinical trials. Therefore, healthcare providers who elect to use Depakote ER for extended periods should continually reevaluate the long-term risk-benefits of the drug for the individual patient.

1.2 Epilepsy

Depakote ER is indicated as monotherapy and adjunctive therapy in the treatment of adult patients and pediatric patients down to the age of 10 years with complex partial seizures that occur either in isolation or in association with other types of seizures. Depakote ER is also indicated for use as sole and adjunctive therapy in the treatment of simple and complex absence seizures in adults and children 10 years of age or older, and adjunctively in adults and children 10 years of age or older with multiple seizure types that include absence seizures.

Simple absence is defined as very brief clouding of the sensorium or loss of consciousness accompanied by certain generalized epileptic discharges without other detectable clinical signs. Complex absence is the term used when other signs are also present.

1.3 Migraine

Depakote ER is indicated for prophylaxis of migraine headaches. There is no evidence that Depakote ER is useful in the acute treatment of migraine headaches.

1.4 Important Limitations

Because of the risk to the fetus of decreased IQ, neurodevelopmental disorders, neural tube defects, and other major congenital malformations, which may occur very early in pregnancy, valproate should not be used to treat women with epilepsy or bipolar disorder who are pregnant or who plan to become pregnant unless other medications have failed to provide adequate symptom control or are otherwise unacceptable. Valproate should not be administered to a woman of childbearing potential unless other medications have failed to provide adequate symptom control or are otherwise unacceptable [see Warnings and Precautions (5.2, 5.3, 5.4), Use in Specific Populations (8.1), and Patient Counseling Information (17)].

For prophylaxis of migraine headaches, Depakote ER is contraindicated in women who are pregnant and in women of childbearing potential who are not using effective contraception [see Contraindications (4)].

2 DOSAGE AND ADMINISTRATION

Depakote ER is an extended-release product intended for once-a-day oral administration. Depakote ER tablets should be swallowed whole and should not be crushed or chewed.

2.1 Mania

Depakote ER tablets are administered orally. The recommended initial dose is 25 mg/kg/day given once daily. The dose should be increased as rapidly as possible to achieve the lowest therapeutic dose which produces the desired clinical effect or the desired range of plasma concentrations. In a placebo-controlled clinical trial of acute mania or mixed type, patients were dosed to a clinical response with a trough plasma concentration between 85 and 125 mcg/mL. The maximum recommended dosage is 60 mg/kg/day.

There is no body of evidence available from controlled trials to guide a clinician in the longer term management of a patient who improves during Depakote ER treatment of an acute manic episode. While it is generally agreed that pharmacological treatment beyond an acute response in mania is desirable, both for maintenance of the initial response and for prevention of new manic episodes, there are no data to support the benefits of Depakote ER in such longer-term treatment (i.e., beyond 3 weeks).

2.2 Epilepsy

Depakote ER (divalproex sodium) extended-release tablets are administered orally, and must be swallowed whole. As Depakote ER dosage is titrated upward, concentrations of clonazepam, diazepam, ethosuximide, lamotrigine, tolbutamide, phenobarbital, carbamazepine, and/or phenytoin may be affected [see Drug Interactions (7.2)].

Complex Partial Seizures

For adults and children 10 years of age or older.

Monotherapy (Initial Therapy)

Depakote ER has not been systematically studied as initial therapy. Patients should initiate therapy at 10 to 15 mg/kg/day. The dosage should be increased by 5 to 10 mg/kg/week to achieve optimal clinical response. Ordinarily, optimal clinical response is achieved at daily doses below 60 mg/kg/day. If satisfactory clinical response has not been achieved, plasma levels should be measured to determine whether or not they are in the usually accepted therapeutic range (50 to 100 mcg/mL). No recommendation regarding the safety of valproate for use at doses above 60 mg/kg/day can be made.

The probability of thrombocytopenia increases significantly at total trough valproate plasma concentrations above 110 mcg/mL in females and 135 mcg/mL in males. The benefit of improved seizure control with higher doses should be weighed against the possibility of a greater incidence of adverse reactions.

Conversion to Monotherapy

Patients should initiate therapy at 10 to 15 mg/kg/day. The dosage should be increased by 5 to 10 mg/kg/week to achieve optimal clinical response. Ordinarily, optimal clinical response is achieved at daily doses below 60 mg/kg/day. If satisfactory clinical response has not been achieved, plasma levels should be measured to determine whether or not they are in the usually accepted therapeutic range (50 - 100 mcg/mL). No recommendation regarding the safety of valproate for use at doses above 60 mg/kg/day can be made.

Concomitant antiepilepsy drug (AED) dosage can ordinarily be reduced by approximately 25% every 2 weeks. This reduction may be started at initiation of Depakote ER therapy, or delayed by 1 to 2 weeks if there is a concern that seizures are likely to occur with a reduction. The speed and duration of withdrawal of the concomitant AED can be highly variable, and patients should be monitored closely during this period for increased seizure frequency.

Adjunctive Therapy

Depakote ER may be added to the patient's regimen at a dosage of 10 to 15 mg/kg/day. The dosage may be increased by 5 to 10 mg/kg/week to achieve optimal clinical response. Ordinarily, optimal clinical response is achieved at daily doses below 60 mg/kg/day. If satisfactory clinical response has not been achieved, plasma levels should be measured to determine whether or not they are in the usually accepted therapeutic range (50 to 100 mcg/mL). No recommendation regarding the safety of valproate for use at doses above 60 mg/kg/day can be made.

In a study of adjunctive therapy for complex partial seizures in which patients were receiving either carbamazepine or phenytoin in addition to valproate, no adjustment of carbamazepine or phenytoin dosage was needed [see Clinical Studies (14.2)]. However, since valproate may interact with these or other concurrently administered AEDs as well as other drugs, periodic plasma concentration determinations of concomitant AEDs are recommended during the early course of therapy [see Drug Interactions (7)].

Simple and Complex Absence Seizures

The recommended initial dose is 15 mg/kg/day, increasing at one week intervals by 5 to 10 mg/kg/day until seizures are controlled or side effects preclude further increases. The maximum recommended dosage is 60 mg/kg/day.

A good correlation has not been established between daily dose, serum concentrations, and therapeutic effect. However, therapeutic valproate serum concentration for most patients with absence seizures is considered to range from 50 to 100 mcg/mL. Some patients may be controlled with lower or higher serum concentrations [see Clinical Pharmacology (12.3)].

As Depakote ER dosage is titrated upward, blood concentrations of phenobarbital and/or phenytoin may be affected [see Drug Interactions (7.2)].

Antiepilepsy drugs should not be abruptly discontinued in patients in whom the drug is administered to prevent major seizures because of the strong possibility of precipitating status epilepticus with attendant hypoxia and threat to life.

2.3 Migraine

Depakote ER is indicated for prophylaxis of migraine headaches in adults.

The recommended starting dose is 500 mg once daily for 1 week, thereafter increasing to 1,000 mg once daily. Although doses other than 1,000 mg once daily of Depakote ER have not been evaluated in patients with migraine, the effective dose range of Depakote (divalproex sodium delayed-release tablets) in these patients is 500-1,000 mg/day. As with other valproate products, doses of Depakote ER should be individualized and dose adjustment may be necessary. If a patient requires smaller dose adjustments than that available with Depakote ER, Depakote should be used instead.

2.4 Conversion from Depakote to Depakote ER

In adult patients and pediatric patients 10 years of age or older with epilepsy previously receiving Depakote, Depakote ER should be administered once-daily using a dose 8 to 20% higher than the total daily dose of Depakote (Table 1). For patients whose Depakote total daily dose cannot be directly converted to Depakote ER, consideration may be given at the clinician’s discretion to increase the patient’s Depakote total daily dose to the next higher dosage before converting to the appropriate total daily dose of Depakote ER.

Table 1. Dose Conversion
Depakote | Depakote ER
Total Daily Dose (mg) | (mg)
500* - 625 | 750
750* - 875 | 1,000
1,000*-1,125 | 1,250
1,250-1,375 | 1,500
1,500-1,625 | 1,750
1,750 | 2,000
1,875-2,000 | 2,250
2,125-2,250 | 2,500
2,375 | 2,750
2,500-2,750 | 3,000
2,875 | 3,250
3,000-3,125 | 3,500
* These total daily doses of Depakote cannot be directly converted to an 8 to 20% higher total daily dose of Depakote ER because the required dosing strengths of Depakote ER are not available. Consideration may be given at the clinician's discretion to increase the patient's Depakote total daily dose to the next higher dosage before converting to the appropriate total daily dose of Depakote ER.

There is insufficient data to allow a conversion factor recommendation for patients with DEPAKOTE doses above 3,125 mg/day. Plasma valproate Cmin concentrations for DEPAKOTE ER on average are equivalent to DEPAKOTE, but may vary across patients after conversion. If satisfactory clinical response has not been achieved, plasma levels should be measured to determine whether or not they are in the usually accepted therapeutic range (50 to 100 mcg/mL) [see Clinical Pharmacology (12.2)].

2.5 General Dosing Advice

Dosing in Elderly Patients

Due to a decrease in unbound clearance of valproate and possibly a greater sensitivity to somnolence in the elderly, the starting dose should be reduced in these patients. Starting doses in the elderly lower than 250 mg can only be achieved by the use of Depakote. Dosage should be increased more slowly and with regular monitoring for fluid and nutritional intake, dehydration, somnolence, and other adverse reactions. Dose reductions or discontinuation of valproate should be considered in patients with decreased food or fluid intake and in patients with excessive somnolence. The ultimate therapeutic dose should be achieved on the basis of both tolerability and clinical response [see Warnings and Precautions (5.16), Use in Specific Populations (8.5), and Clinical Pharmacology (12.3)].

Dose-Related Adverse Reactions

The frequency of adverse effects (particularly elevated liver enzymes and thrombocytopenia) may be dose-related. The probability of thrombocytopenia appears to increase significantly at total valproate concentrations of ≥ 110 mcg/mL (females) or ≥ 135 mcg/mL (males) [see Warnings and Precautions (5.8)]. The benefit of improved therapeutic effect with higher doses should be weighed against the possibility of a greater incidence of adverse reactions.

G.I. Irritation

Patients who experience G.I. irritation may benefit from administration of the drug with food or by slowly building up the dose from an initial low level.

Compliance

Patients should be informed to take Depakote ER every day as prescribed. If a dose is missed it should be taken as soon as possible, unless it is almost time for the next dose. If a dose is skipped, the patient should not double the next dose.

2.6 Dosing in Patients Taking Rufinamide

Patients stabilized on rufinamide before being prescribed valproate should begin valproate therapy at a low dose, and titrate to a clinically effective dose [see Drug Interactions (7.2)].

3 DOSAGE FORMS AND STRENGTHS

Depakote ER 250 mg contains divalproex sodium equivalent to 250 mg of valproic acid in each tablet and is available as:

- White ovaloid tablets with the “a” logo and the code HF
- White ovaloid tablets with the code HF

Depakote ER 500 mg contains divalproex sodium equivalent to 500 mg of valproic acid in each tablet and is available as:

- Gray ovaloid tablets with the “a” logo and the code HC
- Gray ovaloid tablets with the code HC

4 CONTRAINDICATIONS

Depakote ER is contraindicated in patients:

• with hepatic disease or significant hepatic dysfunction [see Warnings and Precautions (5.1)].

• known to have mitochondrial disorders caused by mutations in mitochondrial DNA polymerase γ (POLG; e.g., Alpers-Huttenlocher Syndrome) and children under two years of age who are suspected of having a POLG-related disorder [see Warnings and Precautions (5.1)].

• with known hypersensitivity to divalproex sodium, sodium valproate, or valproic acid. Reactions have included multiorgan hypersensitivity, serious dermatologic reactions, and angioedema [see Warnings and Precautions (5.12, 5.13, 5.14)].

• with known urea cycle disorders [see Warnings and Precautions (5.6)].

• being treated for prophylaxis of migraine headaches: who are pregnant or in women of childbearing potential who are not using effective contraception [see Warnings and Precautions (5.2, 5.3, 5.4) and Use in Specific Populations (8.1)].

5 WARNINGS AND PRECAUTIONS

5.1 Hepatotoxicity

General Information on Hepatotoxicity

Hepatic failure resulting in fatalities has occurred in patients receiving valproate. These incidents usually have occurred during the first six months of treatment. Serious or fatal hepatotoxicity may be preceded by non-specific symptoms such as malaise, weakness, lethargy, facial edema, anorexia, and vomiting. In patients with epilepsy, a loss of seizure control may also occur. Patients should be monitored closely for appearance of these symptoms. Serum liver tests should be performed prior to therapy and at frequent intervals thereafter, especially during the first six months of valproate therapy. However, healthcare providers should not rely totally on serum biochemistry since these tests may not be abnormal in all instances, but should also consider the results of careful interim medical history and physical examination.

Caution should be observed when administering valproate products to patients with a prior history of hepatic disease. Patients on multiple anticonvulsants, children, those with congenital metabolic disorders, those with severe seizure disorders accompanied by mental retardation, and those with organic brain disease may be at particular risk. See below, “Patients with Known or Suspected Mitochondrial Disease.”

Experience has indicated that children under the age of two years are at a considerably increased risk of developing fatal hepatotoxicity, especially those with the aforementioned conditions. When Depakote ER is used in this patient group, it should be used with extreme caution and as a sole agent. The benefits of therapy should be weighed against the risks. In progressively older patient groups experience in epilepsy has indicated that the incidence of fatal hepatotoxicity decreases considerably.

Patients with Known or Suspected Mitochondrial Disease

Depakote ER is contraindicated in patients known to have mitochondrial disorders caused by POLG mutations and children under two years of age who are clinically suspected of having a mitochondrial disorder [see Contraindications (4)]. Valproate-induced acute liver failure and liver-related deaths have been reported in patients with hereditary neurometabolic syndromes caused by mutations in the gene for mitochondrial DNA polymerase γ (POLG) (e.g., Alpers-Huttenlocher Syndrome) at a higher rate than those without these syndromes. Most of the reported cases of liver failure in patients with these syndromes have been identified in children and adolescents.

POLG-related disorders should be suspected in patients with a family history or suggestive symptoms of a POLG-related disorder, including but not limited to unexplained encephalopathy, refractory epilepsy (focal, myoclonic), status epilepticus at presentation, developmental delays, psychomotor regression, axonal sensorimotor neuropathy, myopathy cerebellar ataxia, ophthalmoplegia, or complicated migraine with occipital aura. POLG mutation testing should be performed in accordance with current clinical practice for the diagnostic evaluation of such disorders. The A467T and W748S mutations are present in approximately 2/3 of patients with autosomal recessive POLG-related disorders.

In patients over two years of age who are clinically suspected of having a hereditary mitochondrial disease, Depakote ER should only be used after other anticonvulsants have failed. This older group of patients should be closely monitored during treatment with Depakote ER for the development of acute liver injury with regular clinical assessments and serum liver test monitoring.

The drug should be discontinued immediately in the presence of significant hepatic dysfunction, suspected or apparent. In some cases, hepatic dysfunction has progressed in spite of discontinuation of drug [see Boxed Warning and Contraindications (4)].

5.2 Structural Birth Defects

Valproate can cause fetal harm when administered to a pregnant woman. Pregnancy registry data show that maternal valproate use can cause neural tube defects and other structural abnormalities (e.g., craniofacial defects, cardiovascular malformations, hypospadias, limb malformations). The rate of congenital malformations among babies born to mothers using valproate is about four times higher than the rate among babies born to epileptic mothers using other anti-seizure monotherapies. Evidence suggests that folic acid supplementation prior to conception and during the first trimester of pregnancy decreases the risk for congenital neural tube defects in the general population [see Use in Specific Populations (8.1)].

5.3 Decreased IQ Following in utero Exposure

Valproate can cause decreased IQ scores following in utero exposure. Published epidemiological studies have indicated that children exposed to valproate in utero have lower cognitive test scores than children exposed in utero to either another antiepileptic drug or to no antiepileptic drugs. The largest of these studies^1 is a prospective cohort study conducted in the United States and United Kingdom that found that children with prenatal exposure to valproate (n=62) had lower IQ scores at age 6 (97 [95% C.I. 94-101]) than children with prenatal exposure to the other antiepileptic drug monotherapy treatments evaluated: lamotrigine (108 [95% C.I. 105–110]), carbamazepine (105 [95% C.I. 102–108]), and phenytoin (108 [95% C.I. 104–112]). It is not known when during pregnancy cognitive effects in valproate-exposed children occur. Because the women in this study were exposed to antiepileptic drugs throughout pregnancy, whether the risk for decreased IQ was related to a particular time period during pregnancy could not be assessed.

Although all of the available studies have methodological limitations, the weight of the evidence supports the conclusion that valproate exposure in utero can cause decreased IQ in children.

In animal studies, offspring with prenatal exposure to valproate had malformations similar to those seen in humans and demonstrated neurobehavioral deficits [see Use in Specific Populations (8.1)].

5.4 Use in Women of Childbearing Potential

Because of the risk to the fetus of decreased IQ, neurodevelopmental disorders, and major congenital malformations (including neural tube defects), which may occur very early in pregnancy, valproate should not be administered to a woman of childbearing potential unless other medications have failed to provide adequate symptom control or are otherwise unacceptable. This is especially important when valproate use is considered for a condition not usually associated with permanent injury or death such as prophylaxis of migraine headaches [see Contraindications (4)]. Women should use effective contraception while using valproate.

Women of childbearing potential should be counseled regularly regarding the relative risks and benefits of valproate use during pregnancy. This is especially important for women planning a pregnancy and for girls at the onset of puberty; alternative therapeutic options should be considered for these patients [see Boxed Warning and Use in Specific Populations (8.1)].

To prevent major seizures, valproate should not be discontinued abruptly, as this can precipitate status epilepticus with resulting maternal and fetal hypoxia and threat to life.

Evidence suggests that folic acid supplementation prior to conception and during the first trimester of pregnancy decreases the risk for congenital neural tube defects in the general population. It is not known whether the risk of neural tube defects or decreased IQ in the offspring of women receiving valproate is reduced by folic acid supplementation. Dietary folic acid supplementation both prior to conception and during pregnancy should be routinely recommended for patients using valproate.

5.5 Pancreatitis

Cases of life-threatening pancreatitis have been reported in both children and adults receiving valproate. Some of the cases have been described as hemorrhagic with rapid progression from initial symptoms to death. Some cases have occurred shortly after initial use as well as after several years of use. The rate based upon the reported cases exceeds that expected in the general population and there have been cases in which pancreatitis recurred after rechallenge with valproate. In clinical trials, there were 2 cases of pancreatitis without alternative etiology in 2,416 patients, representing 1,044 patient-years experience. Patients and guardians should be warned that abdominal pain, nausea, vomiting, and/or anorexia can be symptoms of pancreatitis that require prompt medical evaluation. If pancreatitis is diagnosed, Depakote ER should ordinarily be discontinued. Alternative treatment for the underlying medical condition should be initiated as clinically indicated [see Boxed Warning].

5.6 Urea Cycle Disorders

Depakote ER is contraindicated in patients with known urea cycle disorders (UCD).

Hyperammonemic encephalopathy, sometimes fatal, has been reported following initiation of valproate therapy in patients with urea cycle disorders, a group of uncommon genetic abnormalities, particularly ornithine transcarbamylase deficiency. Prior to the initiation of Depakote ER therapy, evaluation for UCD should be considered in the following patients: 1) those with a history of unexplained encephalopathy or coma, encephalopathy associated with a protein load, pregnancy-related or postpartum encephalopathy, unexplained mental retardation, or history of elevated plasma ammonia or glutamine; 2) those with cyclical vomiting and lethargy, episodic extreme irritability, ataxia, low BUN, or protein avoidance; 3) those with a family history of UCD or a family history of unexplained infant deaths (particularly males); 4) those with other signs or symptoms of UCD. Patients who develop symptoms of unexplained hyperammonemic encephalopathy while receiving valproate therapy should receive prompt treatment (including discontinuation of valproate therapy) and be evaluated for underlying urea cycle disorders [see Contraindications (4) and Warnings and Precautions (5.10)].

5.7 Suicidal Behavior and Ideation

Antiepileptic drugs (AEDs), including Depakote ER, increase the risk of suicidal thoughts or behavior in patients taking these drugs for any indication. Patients treated with any AED for any indication should be monitored for the emergence or worsening of depression, suicidal thoughts or behavior, and/or any unusual changes in mood or behavior.

Pooled analyses of 199 placebo-controlled clinical trials (mono- and adjunctive therapy) of 11 different AEDs showed that patients randomized to one of the AEDs had approximately twice the risk (adjusted Relative Risk 1.8, 95% CI:1.2, 2.7) of suicidal thinking or behavior compared to patients randomized to placebo. In these trials, which had a median treatment duration of 12 weeks, the estimated incidence rate of suicidal behavior or ideation among 27,863 AED-treated patients was 0.43%, compared to 0.24% among 16,029 placebo-treated patients, representing an increase of approximately one case of suicidal thinking or behavior for every 530 patients treated. There were four suicides in drug-treated patients in the trials and none in placebo-treated patients, but the number is too small to allow any conclusion about drug effect on suicide.

The increased risk of suicidal thoughts or behavior with AEDs was observed as early as one week after starting drug treatment with AEDs and persisted for the duration of treatment assessed. Because most trials included in the analysis did not extend beyond 24 weeks, the risk of suicidal thoughts or behavior beyond 24 weeks could not be assessed.

The risk of suicidal thoughts or behavior was generally consistent among drugs in the data analyzed. The finding of increased risk with AEDs of varying mechanisms of action and across a range of indications suggests that the risk applies to all AEDs used for any indication. The risk did not vary substantially by age (5-100 years) in the clinical trials analyzed.

Table 2 shows absolute and relative risk by indication for all evaluated AEDs.

Table 2. Risk by Indication for Antiepileptic Drugs in the Pooled Analysis
Indication | Placebo Patients with Events Per 1,000 Patients | Drug Patients with Events Per 1,000 Patients | Relative Risk: Incidence of Events in Drug Patients/Incidence in Placebo Patients | Risk Difference: Additional Drug Patients with Events Per 1,000 Patients
Epilepsy | 1.0 | 3.4 | 3.5 | 2.4
Psychiatric | 5.7 | 8.5 | 1.5 | 2.9
Other | 1.0 | 1.8 | 1.9 | 0.9
Total | 2.4 | 4.3 | 1.8 | 1.9

The relative risk for suicidal thoughts or behavior was higher in clinical trials for epilepsy than in clinical trials for psychiatric or other conditions, but the absolute risk differences were similar for the epilepsy and psychiatric indications.

Anyone considering prescribing Depakote ER or any other AED must balance the risk of suicidal thoughts or behavior with the risk of untreated illness. Epilepsy and many other illnesses for which AEDs are prescribed are themselves associated with morbidity and mortality and an increased risk of suicidal thoughts and behavior. Should suicidal thoughts and behavior emerge during treatment, the prescriber needs to consider whether the emergence of these symptoms in any given patient may be related to the illness being treated.

5.8 Bleeding and Other Hematopoietic Disorders

Valproate is associated with dose-related thrombocytopenia. In a clinical trial of valproate as monotherapy in patients with epilepsy, 34/126 patients (27%) receiving approximately 50 mg/kg/day on average, had at least one value of platelets ≤ 75 x 10^9/L. Approximately half of these patients had treatment discontinued, with return of platelet counts to normal. In the remaining patients, platelet counts normalized with continued treatment. In this study, the probability of thrombocytopenia appeared to increase significantly at total valproate concentrations of ≥ 110 mcg/mL (females) or ≥ 135 mcg/mL (males). The therapeutic benefit which may accompany the higher doses should therefore be weighed against the possibility of a greater incidence of adverse effects. Valproate use has also been associated with decreases in other cell lines and myelodysplasia.

Because of reports of cytopenias, inhibition of the secondary phase of platelet aggregation, and abnormal coagulation parameters, (e.g., low fibrinogen, coagulation factor deficiencies, acquired von Willebrand’s disease), measurements of complete blood counts and coagulation tests are recommended before initiating therapy and at periodic intervals. It is recommended that patients receiving Depakote ER be monitored for blood counts and coagulation parameters prior to planned surgery and during pregnancy [see Use in Specific Populations (8.1)]. Evidence of hemorrhage, bruising, or a disorder of hemostasis/coagulation is an indication for reduction of the dosage or withdrawal of therapy.

5.9 Hyperammonemia

Hyperammonemia has been reported in association with valproate therapy and may be present despite normal liver function tests. In patients who develop unexplained lethargy and vomiting or changes in mental status, hyperammonemic encephalopathy should be considered and an ammonia level should be measured. Hyperammonemia should also be considered in patients who present with hypothermia [see Warnings and Precautions (5.11)]. If ammonia is increased, valproate therapy should be discontinued. Appropriate interventions for treatment of hyperammonemia should be initiated, and such patients should undergo investigation for underlying urea cycle disorders [see Contraindications (4) and Warnings and Precautions (5.6, 5.10)].

During the placebo controlled pediatric mania trial, one (1) in twenty (20) adolescents (5%) treated with valproate developed increased plasma ammonia levels compared to no (0) patients treated with placebo.

Asymptomatic elevations of ammonia are more common and when present, require close monitoring of plasma ammonia levels. If the elevation persists, discontinuation of valproate therapy should be considered.

5.10 Hyperammonemia and Encephalopathy Associated with Concomitant Topiramate Use

Concomitant administration of topiramate and valproate has been associated with hyperammonemia with or without encephalopathy in patients who have tolerated either drug alone. Clinical symptoms of hyperammonemic encephalopathy often include acute alterations in level of consciousness and/or cognitive function with lethargy or vomiting. Hypothermia can also be a manifestation of hyperammonemia [see Warnings and Precautions (5.11)]. In most cases, symptoms and signs abated with discontinuation of either drug. This adverse reaction is not due to a pharmacokinetic interaction. Patients with inborn errors of metabolism or reduced hepatic mitochondrial activity may be at an increased risk for hyperammonemia with or without encephalopathy. Although not studied, an interaction of topiramate and valproate may exacerbate existing defects or unmask deficiencies in susceptible persons. In patients who develop unexplained lethargy, vomiting, or changes in mental status, hyperammonemic encephalopathy should be considered and an ammonia level should be measured [see Contraindications (4) and Warnings and Precautions (5.6, 5.9)].

5.11 Hypothermia

Hypothermia, defined as an unintentional drop in body core temperature to < 35°C (95°F), has been reported in association with valproate therapy both in conjunction with and in the absence of hyperammonemia. This adverse reaction can also occur in patients using concomitant topiramate with valproate after starting topiramate treatment or after increasing the daily dose of topiramate [see Drug Interactions (7.3)]. Consideration should be given to stopping valproate in patients who develop hypothermia, which may be manifested by a variety of clinical abnormalities including lethargy, confusion, coma, and significant alterations in other major organ systems such as the cardiovascular and respiratory systems. Clinical management and assessment should include examination of blood ammonia levels.

5.12 Drug Reaction with Eosinophilia and Systemic Symptoms (DRESS)/Multiorgan Hypersensitivity Reactions

Drug Reaction with Eosinophilia and Systemic Symptoms (DRESS), also known as multiorgan hypersensitivity, has been reported in patients taking valproate. DRESS may be fatal or life-threatening. DRESS typically, although not exclusively, presents with fever, rash, lymphadenopathy, and/or facial swelling, in association with other organ system involvement, such as hepatitis, nephritis, hematological abnormalities, myocarditis, or myositis sometimes resembling an acute viral infection. Eosinophilia is often present. Because this disorder is variable in its expression, other organ systems not noted here may be involved. It is important to note that early manifestations of hypersensitivity, such as fever or lymphadenopathy, may be present even though rash is not evident. If such signs or symptoms are present, the patient should be evaluated immediately. Valproate should be discontinued if an alternative etiology for the signs or symptoms cannot be established.

5.13 Serious Dermatologic Reactions

Serious and sometimes fatal dermatologic reactions, including toxic epidermal necrolysis (TEN), Stevens Johnson syndrome (SJS), Acute Generalized Exanthematous Pustulosis (AGEP), and Erythema Multiforme (EM) have been reported with valproate treatment. Valproate should be discontinued at the first sign of a rash, unless the rash is clearly not drug related. If a rash occurs, the patient should be evaluated for signs and symptoms of Drug Reaction with Eosinophilia and Systemic Symptoms (DRESS) [see Warnings and Precautions (5.12)]. If signs or symptoms suggest TEN/SJS/AGEP/EM, use of this drug should not be resumed and alternative therapy should be considered.

5.14 Angioedema

Angioedema has been reported in patients treated with valproate in the postmarketing setting. Valproate should be discontinued immediately if symptoms of angioedema, such as facial, perioral, or upper airway swelling occur. Valproate should be discontinued permanently if a clear alternative etiology for the reaction cannot be established [see Contraindications (4)].

5.15 Interaction with Carbapenem Antibiotics

Carbapenem antibiotics (for example, ertapenem, imipenem, meropenem; this is not a complete list) may reduce serum valproate concentrations to subtherapeutic levels, resulting in loss of seizure control. Serum valproate concentrations should be monitored frequently after initiating carbapenem therapy. Alternative antibacterial or anticonvulsant therapy should be considered if serum valproate concentrations drop significantly or seizure control deteriorates [see Drug Interactions (7.1)].

5.16 Somnolence in the Elderly

In a double-blind, multicenter trial of valproate in elderly patients with dementia (mean age = 83 years), doses were increased by 125 mg/day to a target dose of 20 mg/kg/day. A significantly higher proportion of valproate patients had somnolence compared to placebo, and although not statistically significant, there was a higher proportion of patients with dehydration. Discontinuations for somnolence were also significantly higher than with placebo. In some patients with somnolence (approximately one-half), there was associated reduced nutritional intake and weight loss. There was a trend for the patients who experienced these events to have a lower baseline albumin concentration, lower valproate clearance, and a higher BUN. In elderly patients, dosage should be increased more slowly and with regular monitoring for fluid and nutritional intake, dehydration, somnolence, and other adverse reactions. Dose reductions or discontinuation of valproate should be considered in patients with decreased food or fluid intake and in patients with excessive somnolence [see Dosage and Administration (2.4)].

5.17 Monitoring: Drug Plasma Concentration

Since valproate may interact with concurrently administered drugs which are capable of enzyme induction, periodic plasma concentration determinations of valproate and concomitant drugs are recommended during the early course of therapy [see Drug Interactions (7)].

5.18 Effect on Ketone and Thyroid Function Tests

Valproate is partially eliminated in the urine as a keto-metabolite which may lead to a false interpretation of the urine ketone test.

There have been reports of altered thyroid function tests associated with valproate. The clinical significance of these is unknown.

5.19 Effect on HIV and CMV Viruses Replication

There are in vitro studies that suggest valproate stimulates the replication of the HIV and CMV viruses under certain experimental conditions. The clinical consequence, if any, is not known. Additionally, the relevance of these in vitro findings is uncertain for patients receiving maximally suppressive antiretroviral therapy. Nevertheless, these data should be borne in mind when interpreting the results from regular monitoring of the viral load in HIV infected patients receiving valproate or when following CMV infected patients clinically.

5.20 Medication Residue in the Stool

There have been rare reports of medication residue in the stool. Some patients have had anatomic (including ileostomy or colostomy) or functional gastrointestinal disorders with shortened GI transit times. In some reports, medication residues have occurred in the context of diarrhea. It is recommended that plasma valproate levels be checked in patients who experience medication residue in the stool, and patients’ clinical condition should be monitored. If clinically indicated, alternative treatment may be considered.

6 ADVERSE REACTIONS

The following serious adverse reactions are described below and elsewhere in the labeling:

- Hepatic Failure [see Warnings and Precautions (5.1)]
- Birth Defects [see Warnings and Precautions (5.2)]
- Decreased IQ following in utero exposure [see Warnings and Precautions (5.3)]
- Pancreatitis [see Warnings and Precautions (5.5)]
- Hyperammonemic Encephalopathy [see Warnings and Precautions (5.6, 5.9, 5.10)]
- Suicidal Behavior and Ideation [see Warnings and Precautions (5.7)]
- Bleeding and Other Hematopoietic Disorders [see Warnings and Precautions (5.8)]
- Hypothermia [see Warnings and Precautions (5.11)]
- Drug Reaction with Eosinophilia and Systemic Symptoms (DRESS)/Multiorgan Hypersensitivity Reactions [see Warnings and Precautions (5.12)]
- Serious Dermatologic Reactions [see Warnings and Precautions (5.13)]
- Angioedema [see Warnings and Precautions (5.14)]
- Somnolence in the Elderly [see Warnings and Precautions (5.16)]

Because clinical studies are conducted under widely varying conditions, adverse reaction rates observed in the clinical studies of a drug cannot be directly compared to rates in the clinical studies of another drug and may not reflect the rates observed in practice.

Information on pediatric adverse reactions is presented in section 8.

6.1 Mania

The incidence of treatment-emergent events has been ascertained based on combined data from two three week placebo-controlled clinical trials of Depakote ER in the treatment of manic episodes associated with bipolar disorder.

Table 3 summarizes those adverse reactions reported for patients in these trials where the incidence rate in the Depakote ER-treated group was greater than 5% and greater than the placebo incidence.

Table 3. Adverse Reactions Reported by > 5% of Depakote-Treated Patients During
Placebo-Controlled Trials of Acute Mania^1
Adverse Event | Depakote ER (n=338) % | Placebo (n=263) %
Somnolence | 26 | 14
Dyspepsia | 23 | 11
Nausea | 19 | 13
Vomiting | 13 | 5
Diarrhea | 12 | 8
Dizziness | 12 | 7
Pain | 11 | 10
Abdominal Pain | 10 | 5
Accidental Injury | 6 | 5
Asthenia | 6 | 5
Pharyngitis | 6 | 5
^1 The following adverse reactions/event occurred at an equal or greater incidence for placebo than for Depakote ER: headache

The following additional adverse reactions were reported by greater than 1% of the Depakote ER-treated patients in controlled clinical trials:

Body as a Whole: Back Pain, Chills, Chills and Fever, Drug Level Increased, Flu Syndrome, Infection, Infection Fungal, Neck Rigidity.

Cardiovascular System: Arrhythmia, Hypertension, Hypotension, Postural Hypotension.

Digestive System: Constipation, Dry Mouth, Dysphagia, Fecal Incontinence, Flatulence, Gastroenteritis, Glossitis, Gum Hemorrhage, Mouth Ulceration.

Hemic and Lymphatic System: Anemia, Bleeding Time Increased, Ecchymosis, Leucopenia.

Metabolic and Nutritional Disorders: Hypoproteinemia, Peripheral Edema.

Musculoskeletal System: Arthrosis, Myalgia.

Nervous System: Abnormal Gait, Agitation, Catatonic Reaction, Dysarthria, Hallucinations, Hypertonia, Hypokinesia, Psychosis, Reflexes Increased, Sleep Disorder, Tardive Dyskinesia, Tremor.

Respiratory System: Hiccup, Rhinitis.

Skin and Appendages: Discoid Lupus Erythematosus, Erythema Nodosum, Furunculosis, Maculopapular Rash, Pruritus, Rash, Seborrhea, Sweating, Vesiculobullous Rash.

Special Senses: Conjunctivitis, Dry Eyes, Eye Disorder, Eye Pain, Photophobia, Taste Perversion.

Urogenital System: Cystitis, Urinary Tract Infection, Menstrual Disorder, Vaginitis.

6.2 Epilepsy

Based on a placebo-controlled trial of adjunctive therapy for treatment of complex partial seizures, Depakote was generally well tolerated with most adverse reactions rated as mild to moderate in severity. Intolerance was the primary reason for discontinuation in the Depakote-treated patients (6%), compared to 1% of placebo-treated patients.

Table 4 lists treatment-emergent adverse reactions which were reported by ≥ 5% of Depakote-treated patients and for which the incidence was greater than in the placebo group, in the placebo-controlled trial of adjunctive therapy for treatment of complex partial seizures. Since patients were also treated with other antiepilepsy drugs, it is not possible, in most cases, to determine whether the following adverse reactions can be ascribed to Depakote alone, or the combination of Depakote and other antiepilepsy drugs.

Table 4. Adverse Reactions Reported by ≥ 5% of Patients Treated with Valproate During Placebo-Controlled Trial of Adjunctive Therapy for Complex Partial Seizures
Body System/Event | Depakote (N=77) % | Placebo (N=70) %
Body as a Whole
Headache | 31 | 21
Asthenia | 27 | 7
Fever | 6 | 4
Gastrointestinal System
Nausea | 48 | 14
Vomiting | 27 | 7
Abdominal Pain | 23 | 6
Diarrhea | 13 | 6
Anorexia | 12 | 0
Dyspepsia | 8 | 4
Constipation | 5 | 1
Nervous System
Somnolence | 27 | 11
Tremor | 25 | 6
Dizziness | 25 | 13
Diplopia | 16 | 9
Amblyopia/Blurred Vision | 12 | 9
Ataxia | 8 | 1
Nystagmus | 8 | 1
Emotional Lability | 6 | 4
Thinking Abnormal | 6 | 0
Amnesia | 5 | 1
Respiratory System
Flu Syndrome | 12 | 9
Infection | 12 | 6
Bronchitis | 5 | 1
Rhinitis | 5 | 4
Other
Alopecia | 6 | 1
Weight Loss | 6 | 0

Table 5 lists treatment-emergent adverse reactions which were reported by ≥ 5% of patients in the high dose valproate group, and for which the incidence was greater than in the low dose group, in a controlled trial of Depakote monotherapy treatment of complex partial seizures. Since patients were being titrated off another antiepilepsy drug during the first portion of the trial, it is not possible, in many cases, to determine whether the following adverse reactions can be ascribed to Depakote alone, or the combination of valproate and other antiepilepsy drugs.

Table 5. Adverse Reactions Reported by ≥ 5% of Patients in the High Dose Group in the Controlled Trial of Valproate Monotherapy for Complex Partial Seizures^1
Body System/Event | High Dose (n=131) % | Low Dose (n=134) %
Body as a Whole
Asthenia | 21 | 10
Digestive System
Nausea | 34 | 26
Diarrhea | 23 | 19
Vomiting | 23 | 15
Abdominal Pain | 12 | 9
Anorexia | 11 | 4
Dyspepsia | 11 | 10
Hemic/Lymphatic System
Thrombocytopenia | 24 | 1
Ecchymosis | 5 | 4
Metabolic/Nutritional
Weight Gain | 9 | 4
Peripheral Edema | 8 | 3
Nervous System
Tremor | 57 | 19
Somnolence | 30 | 18
Dizziness | 18 | 13
Insomnia | 15 | 9
Nervousness | 11 | 7
Amnesia | 7 | 4
Nystagmus | 7 | 1
Depression | 5 | 4
Respiratory System
Infection | 20 | 13
Pharyngitis | 8 | 2
Dyspnea | 5 | 1
Skin and Appendages
Alopecia | 24 | 13
Special Senses
Amblyopia/Blurred Vision | 8 | 4
Tinnitus | 7 | 1
^1 Headache was the only adverse event that occurred in ≥5% of patients in the high dose group and at an equal or greater incidence in the low dose group.

The following additional adverse reactions were reported by greater than 1% but less than 5% of the 358 patients treated with valproate in the controlled trials of complex partial seizures:

Body as a Whole: Back pain, chest pain, malaise.

Cardiovascular System: Tachycardia, hypertension, palpitation.

Digestive System: Increased appetite, flatulence, hematemesis, eructation, pancreatitis, periodontal abscess.

Hemic and Lymphatic System: Petechia.

Metabolic and Nutritional Disorders: SGOT increased, SGPT increased.

Musculoskeletal System: Myalgia, twitching, arthralgia, leg cramps, myasthenia.

Nervous System: Anxiety, confusion, abnormal gait, paresthesia, hypertonia, incoordination, abnormal dreams, personality disorder.

Respiratory System: Sinusitis, cough increased, pneumonia, epistaxis.

Skin and Appendages: Rash, pruritus, dry skin.

Special Senses: Taste perversion, abnormal vision, deafness, otitis media.

Urogenital System: Urinary incontinence, vaginitis, dysmenorrhea, amenorrhea, urinary frequency.

6.3 Migraine

Based on two placebo-controlled clinical trials and their long term extension, valproate was generally well tolerated with most adverse reactions rated as mild to moderate in severity. Of the 202 patients exposed to valproate in the placebo-controlled trials, 17% discontinued for intolerance. This is compared to a rate of 5% for the 81 placebo patients. Including the long term extension study, the adverse reactions reported as the primary reason for discontinuation by ≥ 1% of 248 valproate-treated patients were alopecia (6%), nausea and/or vomiting (5%), weight gain (2%), tremor (2%), somnolence (1%), elevated SGOT and/or SGPT (1%), and depression (1%).

Table 6 includes those adverse reactions reported for patients in the placebo-controlled trial where the incidence rate in the Depakote ER-treated group was greater than 5% and was greater than that for placebo patients.

Table 6. Adverse Reactions Reported by >5% of Depakote ER-Treated Patients During the Migraine Placebo-Controlled Trial with a Greater Incidence than Patients Taking Placebo^1
Body System Event | Depakote ER (n=122) % | Placebo (n=115) %
Gastrointestinal System
Nausea | 15 | 9
Dyspepsia | 7 | 4
Diarrhea | 7 | 3
Vomiting | 7 | 2
Abdominal Pain | 7 | 5
Nervous System
Somnolence | 7 | 2
Other
Infection | 15 | 14
^1 The following adverse reactions occurred in greater than 5% of Depakote ER-treated patients and at a greater incidence for placebo than for Depakote ER: asthenia and flu syndrome.

The following additional adverse reactions were reported by greater than 1% but not more than 5% of Depakote ER-treated patients and with a greater incidence than placebo in the placebo-controlled clinical trial for migraine prophylaxis:

Body as a Whole: Accidental injury, viral infection.

Digestive System: Increased appetite, tooth disorder.

Metabolic and Nutritional Disorders: Edema, weight gain.

Nervous System: Abnormal gait, dizziness, hypertonia, insomnia, nervousness, tremor, vertigo.

Respiratory System: Pharyngitis, rhinitis.

Skin and Appendages: Rash.

Special Senses: Tinnitus.

Table 7 includes those adverse reactions reported for patients in the placebo-controlled trials where the incidence rate in the valproate-treated group was greater than 5% and was greater than that for placebo patients.

Table 7. Adverse Reactions Reported by > 5% of Valproate-Treated Patients During Migraine Placebo-Controlled Trials with a Greater Incidence than Patients Taking Placebo^1
Body System Reaction | Depakote (n=202) % | Placebo (n=81) %
Gastrointestinal System
Nausea | 31 | 10
Dyspepsia | 13 | 9
Diarrhea | 12 | 7
Vomiting | 11 | 1
Abdominal Pain | 9 | 4
Increased Appetite | 6 | 4
Nervous System
Asthenia | 20 | 9
Somnolence | 17 | 5
Dizziness | 12 | 6
Tremor | 9 | 0
Other
Weight Gain | 8 | 2
Back Pain | 8 | 6
Alopecia | 7 | 1
^1 The following adverse reactions occurred in greater than 5% of Depakote-treated patients and at a greater incidence for placebo than for Depakote: flu syndrome and pharyngitis.

The following additional adverse reactions were reported by greater than 1% but not more than 5% of the 202 valproate-treated patients in the controlled clinical trials:

Body as a Whole: Chest pain.

Cardiovascular System: Vasodilatation.

Digestive System: Constipation, dry mouth, flatulence, and stomatitis.

Hemic and Lymphatic System: Ecchymosis.

Metabolic and Nutritional Disorders: Peripheral edema.

Musculoskeletal System: Leg cramps.

Nervous System: Abnormal dreams, confusion, paresthesia, speech disorder, and thinking abnormalities.

Respiratory System: Dyspnea, and sinusitis.

Skin and Appendages: Pruritus.

Urogenital System: Metrorrhagia.

6.4 Postmarketing Experience

The following adverse reactions have been identified during post approval use of Depakote. Because these reactions are reported voluntarily from a population of uncertain size, it is not always possible to reliably estimate their frequency or establish a causal relationship to drug exposure.

Dermatologic: Hair texture changes, hair color changes, photosensitivity, erythema multiforme, toxic epidermal necrolysis, nail and nail bed disorders, Stevens-Johnson syndrome, hyperpigmentation, and acute generalized exanthematous pustulosis [see Warnings and Precautions (5.13)].

Psychiatric: Emotional upset, psychosis, aggression, psychomotor hyperactivity, hostility, disturbance in attention, learning disorder, and behavioral deterioration.

Neurologic: Paradoxical convulsion, parkinsonism

There have been several reports of acute or subacute cognitive decline and behavioral changes (apathy or irritability) with cerebral pseudoatrophy on imaging associated with valproate therapy; both the cognitive/behavioral changes and cerebral pseudoatrophy reversed partially or fully after valproate discontinuation.

There have been reports of acute or subacute encephalopathy in the absence of elevated ammonia levels, elevated valproate levels, or neuroimaging changes. The encephalopathy reversed partially or fully after valproate discontinuation.

Musculoskeletal: Fractures, decreased bone mineral density, osteopenia, osteoporosis, and weakness.

Hematologic: Relative lymphocytosis, macrocytosis, leukopenia, acquired Pelger-Huet anomaly, anemia including macrocytic with or without folate deficiency, bone marrow suppression, pancytopenia, aplastic anemia, agranulocytosis, and acute intermittent porphyria.

Endocrine: Irregular menses, secondary amenorrhea, hyperandrogenism, hirsutism, elevated testosterone level, breast enlargement, galactorrhea, parotid gland swelling, polycystic ovary disease, decreased carnitine concentrations, hyponatremia, hyperglycinemia, and inappropriate ADH secretion.

There have been rare reports of Fanconi's syndrome occurring chiefly in children.

Metabolism and nutrition: Weight gain.

Reproductive: Aspermia, azoospermia, decreased sperm count, decreased spermatozoa motility, male infertility, and abnormal spermatozoa morphology.

Genitourinary: Enuresis, urinary tract infection, and tubulointerstitial nephritis.

Special Senses: Hearing loss.

Other: Allergic reaction, anaphylaxis, developmental delay, bone pain, bradycardia, cutaneous vasculitis, and angioedema [see Warnings and Precautions (5.14)].

7 DRUG INTERACTIONS

7.1 Effects of Co-Administered Drugs on Valproate Clearance

Drugs that affect the level of expression of hepatic enzymes, particularly those that elevate levels of glucuronosyltransferases (such as ritonavir), may increase the clearance of valproate. For example, phenytoin, carbamazepine, and phenobarbital (or primidone) can double the clearance of valproate. Thus, patients on monotherapy will generally have longer half-lives and higher concentrations than patients receiving polytherapy with antiepilepsy drugs.

In contrast, drugs that are inhibitors of cytochrome P450 isozymes, e.g., antidepressants, may be expected to have little effect on valproate clearance because cytochrome P450 microsomal mediated oxidation is a relatively minor secondary metabolic pathway compared to glucuronidation and beta-oxidation.

Because of these changes in valproate clearance, monitoring of valproate and concomitant drug concentrations should be increased whenever enzyme inducing drugs are introduced or withdrawn.

The following list provides information about the potential for an influence of several commonly prescribed medications on valproate pharmacokinetics. The list is not exhaustive nor could it be, since new interactions are continuously being reported.

Drugs for which a potentially important interaction has been observed

Aspirin

A study involving the co-administration of aspirin at antipyretic doses (11 to 16 mg/kg) with valproate to pediatric patients (n=6) revealed a decrease in protein binding and an inhibition of metabolism of valproate. Valproate free fraction was increased 4-fold in the presence of aspirin compared to valproate alone. The β-oxidation pathway consisting of 2-E-valproic acid, 3-OH-valproic acid, and 3-keto valproic acid was decreased from 25% of total metabolites excreted on valproate alone to 8.3% in the presence of aspirin. Whether or not the interaction observed in this study applies to adults is unknown, but caution should be observed if valproate and aspirin are to be co-administered.

Carbapenem Antibiotics

A clinically significant reduction in serum valproic acid concentration has been reported in patients receiving carbapenem antibiotics (for example, ertapenem, imipenem, meropenem; this is not a complete list) and may result in loss of seizure control. The mechanism of this interaction is not well understood. Serum valproic acid concentrations should be monitored frequently after initiating carbapenem therapy. Alternative antibacterial or anticonvulsant therapy should be considered if serum valproic acid concentrations drop significantly or seizure control deteriorates [see Warnings and Precautions (5.15)].

Estrogen-Containing Hormonal Contraceptives

Estrogen-containing hormonal contraceptives may increase the clearance of valproate, which may result in decreased concentration of valproate and potentially increased seizure frequency. Prescribers should monitor serum valproate concentrations and clinical response when adding or discontinuing estrogen containing products.

Felbamate

A study involving the co-administration of 1,200 mg/day of felbamate with valproate to patients with epilepsy (n=10) revealed an increase in mean valproate peak concentration by 35% (from 86 to 115 mcg/mL) compared to valproate alone. Increasing the felbamate dose to 2,400 mg/day increased the mean valproate peak concentration to 133 mcg/mL (another 16% increase). A decrease in valproate dosage may be necessary when felbamate therapy is initiated.

Methotrexate

Methotrexate may decrease serum valproate levels and potentially result in increased frequency of seizures or bipolar symptoms. Prescribers should monitor serum valproate concentrations and clinical response when adding or discontinuing methotrexate and adjust valproate dosage, if necessary.

Rifampin

A study involving the administration of a single dose of valproate (7 mg/kg) 36 hours after 5 nights of daily dosing with rifampin (600 mg) revealed a 40% increase in the oral clearance of valproate. Valproate dosage adjustment may be necessary when it is co-administered with rifampin.

7.2 Effects of Valproate on Other Drugs

Valproate has been found to be a weak inhibitor of some P450 isozymes, epoxide hydrase, and glucuronosyltransferases.

The following list provides information about the potential for an influence of valproate co-administration on the pharmacokinetics or pharmacodynamics of several commonly prescribed medications. The list is not exhaustive, since new interactions are continuously being reported.

Drugs for which a potentially important valproate interaction has been observed

Amitriptyline/Nortriptyline

Administration of a single oral 50 mg dose of amitriptyline to 15 normal volunteers (10 males and 5 females) who received valproate (500 mg BID) resulted in a 21% decrease in plasma clearance of amitriptyline and a 34% decrease in the net clearance of nortriptyline. Rare postmarketing reports of concurrent use of valproate and amitriptyline resulting in an increased amitriptyline level have been received. Concurrent use of valproate and amitriptyline has rarely been associated with toxicity. Monitoring of amitriptyline levels should be considered for patients taking valproate concomitantly with amitriptyline. Consideration should be given to lowering the dose of amitriptyline/nortriptyline in the presence of valproate.

Carbamazepine/carbamazepine-10,11-Epoxide

Serum levels of carbamazepine (CBZ) decreased 17% while that of carbamazepine-10,11-epoxide (CBZ-E) increased by 45% upon co-administration of valproate and CBZ to epileptic patients.

Clonazepam

The concomitant use of valproate and clonazepam may induce absence status in patients with a history of absence type seizures.

Diazepam

Valproate displaces diazepam from its plasma albumin binding sites and inhibits its metabolism. Co-administration of valproate (1,500 mg daily) increased the free fraction of diazepam (10 mg) by 90% in healthy volunteers (n=6). Plasma clearance and volume of distribution for free diazepam were reduced by 25% and 20%, respectively, in the presence of valproate. The elimination half-life of diazepam remained unchanged upon addition of valproate.

Ethosuximide

Valproate inhibits the metabolism of ethosuximide. Administration of a single ethosuximide dose of 500 mg with valproate (800 to 1,600 mg/day) to healthy volunteers (n=6) was accompanied by a 25% increase in elimination half-life of ethosuximide and a 15% decrease in its total clearance as compared to ethosuximide alone. Patients receiving valproate and ethosuximide, especially along with other anticonvulsants, should be monitored for alterations in serum concentrations of both drugs.

Lamotrigine

In a steady-state study involving 10 healthy volunteers, the elimination half-life of lamotrigine increased from 26 to 70 hours with valproate co-administration (a 165% increase). The dose of lamotrigine should be reduced when co-administered with valproate. Serious skin reactions (such as Stevens-Johnson syndrome and toxic epidermal necrolysis) have been reported with concomitant lamotrigine and valproate administration. See lamotrigine package insert for details on lamotrigine dosing with concomitant valproate administration.

Phenobarbital

Valproate was found to inhibit the metabolism of phenobarbital. Co-administration of valproate (250 mg BID for 14 days) with phenobarbital to normal subjects (n=6) resulted in a 50% increase in half-life and a 30% decrease in plasma clearance of phenobarbital (60 mg single-dose). The fraction of phenobarbital dose excreted unchanged increased by 50% in presence of valproate.

There is evidence for severe CNS depression, with or without significant elevations of barbiturate or valproate serum concentrations. All patients receiving concomitant barbiturate therapy should be closely monitored for neurological toxicity. Serum barbiturate concentrations should be obtained, if possible, and the barbiturate dosage decreased, if appropriate.

Primidone, which is metabolized to a barbiturate, may be involved in a similar interaction with valproate.

Phenytoin

Valproate displaces phenytoin from its plasma albumin binding sites and inhibits its hepatic metabolism. Co-administration of valproate (400 mg TID) with phenytoin (250 mg) in normal volunteers (n=7) was associated with a 60% increase in the free fraction of phenytoin. Total plasma clearance and apparent volume of distribution of phenytoin increased 30% in the presence of valproate. Both the clearance and apparent volume of distribution of free phenytoin were reduced by 25%.

In patients with epilepsy, there have been reports of breakthrough seizures occurring with the combination of valproate and phenytoin. The dosage of phenytoin should be adjusted as required by the clinical situation.

Propofol

The concomitant use of valproate and propofol may lead to increased blood levels of propofol. Reduce the dose of propofol when co-administering with valproate. Monitor patients closely for signs of increased sedation or cardiorespiratory depression.

Rufinamide

Based on a population pharmacokinetic analysis, rufinamide clearance was decreased by valproate. Rufinamide concentrations were increased by <16% to 70%, dependent on concentration of valproate (with the larger increases being seen in pediatric patients at high doses or concentrations of valproate). Patients stabilized on rufinamide before being prescribed valproate should begin valproate therapy at a low dose, and titrate to a clinically effective dose [see Dosage and Administration (2.6)]. Similarly, patients on valproate should begin at a rufinamide dose lower than 10 mg/kg per day (pediatric patients) or 400 mg per day (adults).

Tolbutamide

From in vitro experiments, the unbound fraction of tolbutamide was increased from 20% to 50% when added to plasma samples taken from patients treated with valproate. The clinical relevance of this displacement is unknown.

Warfarin

In an in vitro study, valproate increased the unbound fraction of warfarin by up to 32.6%. The therapeutic relevance of this is unknown; however, coagulation tests should be monitored if valproate therapy is instituted in patients taking anticoagulants.

Zidovudine

In six patients who were seropositive for HIV, the clearance of zidovudine (100 mg q8h) was decreased by 38% after administration of valproate (250 or 500 mg q8h); the half-life of zidovudine was unaffected.

7.3 Topiramate

Concomitant administration of valproate and topiramate has been associated with hyperammonemia with and without encephalopathy [see Contraindications (4) and Warnings and Precautions (5.6, 5.9, 5.10)]. Concomitant administration of topiramate with valproate has also been associated with hypothermia in patients who have tolerated either drug alone. It may be prudent to examine blood ammonia levels in patients in whom the onset of hypothermia has been reported [see Warnings and Precautions (5.9, 5.11)].

7.4 Cannabidiol

Concomitant administration of valproate and cannabidiol has been associated with an increased risk of ALT and/or AST elevation. This has been manageable by dose reduction or, in more severe cases, by discontinuation of one or both drugs. Liver function, including serum transaminase and total bilirubin levels, should be monitored during concomitant treatment [see Warnings and Precautions (5.1)].

8 USE IN SPECIFIC POPULATIONS

8.1 Pregnancy

Pregnancy Exposure Registry

There is a pregnancy exposure registry that monitors pregnancy outcomes in women exposed to antiepileptic drugs (AEDs), including Depakote ER, during pregnancy. Encourage women who are taking Depakote ER during pregnancy to enroll in the North American Antiepileptic Drug (NAAED) Pregnancy Registry by calling toll-free 1-888-233-2334 or visiting the website, http://www.aedpregnancyregistry.org/. This must be done by the patient herself.

Risk Summary

For use in prophylaxis of migraine headaches, valproate is contraindicated in women who are pregnant and in women of childbearing potential who are not using effective contraception [see Contraindications (4)].

For use in epilepsy or bipolar disorder, valproate should not be used to treat women who are pregnant or who plan to become pregnant unless other medications have failed to provide adequate symptom control or are otherwise unacceptable [see Boxed Warning and Warnings and Precautions (5.2, 5.3)]. Women with epilepsy who become pregnant while taking valproate should not discontinue valproate abruptly, as this can precipitate status epilepticus with resulting maternal and fetal hypoxia and threat to life.

Maternal valproate use during pregnancy for any indication increases the risk of congenital malformations, particularly neural tube defects including spina bifida, but also malformations involving other body systems (e.g., craniofacial defects including oral clefts, cardiovascular malformations, hypospadias, limb malformations). This risk is dose-dependent; however, a threshold dose below which no risk exists cannot be established. In utero exposure to valproate may also result in hearing impairment or hearing loss. Valproate polytherapy with other AEDs has been associated with an increased frequency of congenital malformations compared with AED monotherapy. The risk of major structural abnormalities is greatest during the first trimester; however, other serious developmental effects can occur with valproate use throughout pregnancy. The rate of congenital malformations among babies born to epileptic mothers who used valproate during pregnancy has been shown to be about four times higher than the rate among babies born to epileptic mothers who used other anti-seizure monotherapies [see Warnings and Precautions (5.2) and Data (Human)].

Epidemiological studies have indicated that children exposed to valproate in utero have lower IQ scores and a higher risk of neurodevelopmental disorders compared to children exposed to either another AED in utero or to no AEDs in utero [see Warnings and Precautions (5.3) and Data (Human)].

An observational study has suggested that exposure to valproate products during pregnancy increases the risk of autism spectrum disorders [see Data (Human)].

In animal studies, valproate administration during pregnancy resulted in fetal structural malformations similar to those seen in humans and neurobehavioral deficits in the offspring at clinically relevant doses [see Data (Animal)].

There have been reports of hypoglycemia in neonates and fatal cases of hepatic failure in infants following maternal use of valproate during pregnancy.

Pregnant women taking valproate may develop hepatic failure or clotting abnormalities including thrombocytopenia, hypofibrinogenemia, and/or decrease in other coagulation factors, which may result in hemorrhagic complications in the neonate including death [see Warnings and Precautions (5.1, 5.8)].

Available prenatal diagnostic testing to detect neural tube and other defects should be offered to pregnant women using valproate.

Evidence suggests that folic acid supplementation prior to conception and during the first trimester of pregnancy decreases the risk for congenital neural tube defects in the general population. It is not known whether the risk of neural tube defects or decreased IQ in the offspring of women receiving valproate is reduced by folic acid supplementation. Dietary folic acid supplementation both prior to conception and during pregnancy should be routinely recommended for patients using valproate [see Warnings and Precautions (5.2, 5.4)].

All pregnancies have a background risk of birth defect, loss, or other adverse outcomes. In the U.S. general population, the estimated background risk of major birth defects and miscarriage in clinically recognized pregnancies is 2 to 4% and 15 to 20%, respectively.

Clinical Considerations

Disease-associated maternal and/or embryo/fetal risk

To prevent major seizures, women with epilepsy should not discontinue valproate abruptly, as this can precipitate status epilepticus with resulting maternal and fetal hypoxia and threat to life. Even minor seizures may pose some hazard to the developing embryo or fetus [see Warnings and Precautions (5.4)]. However, discontinuation of the drug may be considered prior to and during pregnancy in individual cases if the seizure disorder severity and frequency do not pose a serious threat to the patient.

Maternal adverse reactions

Pregnant women taking valproate may develop clotting abnormalities including thrombocytopenia, hypofibrinogenemia, and/or decrease in other coagulation factors, which may result in hemorrhagic complications in the neonate including death [see Warnings and Precautions (5.8)]. If valproate is used in pregnancy, the clotting parameters should be monitored carefully in the mother. If abnormal in the mother, then these parameters should also be monitored in the neonate.

Patients taking valproate may develop hepatic failure [see Boxed Warning and Warnings and Precautions (5.1)]. Fatal cases of hepatic failure in infants exposed to valproate in utero have also been reported following maternal use of valproate during pregnancy.

Hypoglycemia has been reported in neonates whose mothers have taken valproate during pregnancy.

Data

Human

Neural tube defects and other structural abnormalities

There is an extensive body of evidence demonstrating that exposure to valproate in utero increases the risk of neural tube defects and other structural abnormalities. Based on published data from the CDC’s National Birth Defects Prevention Network, the risk of spina bifida in the general population is about 0.06 to 0.07% (6 to 7 in 10,000 births) compared to the risk following in utero valproate exposure estimated to be approximately 1 to 2% (100 to 200 in 10,000 births).

The NAAED Pregnancy Registry has reported a major malformation rate of 9-11% in the offspring of women exposed to an average of 1,000 mg/day of valproate monotherapy during pregnancy. These data show an up to a five-fold increased risk for any major malformation following valproate exposure in utero compared to the risk following exposure in utero to other AEDs taken as monotherapy. The major congenital malformations included cases of neural tube defects, cardiovascular malformations, craniofacial defects (e.g., oral clefts, craniosynostosis), hypospadias, limb malformations (e.g., clubfoot, polydactyly), and other malformations of varying severity involving other body systems [see Warnings and Precautions (5.2)].

Effect on IQ and neurodevelopmental effects

Published epidemiological studies have indicated that children exposed to valproate in utero have lower IQ scores than children exposed to either another AED in utero or to no AEDs in utero. The largest of these studies^1 is a prospective cohort study conducted in the United States and United Kingdom that found that children with prenatal exposure to valproate (n=62) had lower IQ scores at age 6 (97 [95% C.I. 94-101]) than children with prenatal exposure to the other anti-epileptic drug monotherapy treatments evaluated: lamotrigine (108 [95% C.I. 105–110]), carbamazepine (105 [95% C.I. 102–108]) and phenytoin (108 [95% C.I. 104–112]). It is not known when during pregnancy cognitive effects in valproate-exposed children occur. Because the women in this study were exposed to AEDs throughout pregnancy, whether the risk for decreased IQ was related to a particular time period during pregnancy could not be assessed [see Warnings and Precautions (5.3)].

Although the available studies have methodological limitations, the weight of the evidence supports a causal association between valproate exposure in utero and subsequent adverse effects on neurodevelopment, including increases in autism spectrum disorders and attention deficit/hyperactivity disorder (ADHD). An observational study has suggested that exposure to valproate products during pregnancy increases the risk of autism spectrum disorders. In this study, children born to mothers who had used valproate products during pregnancy had 2.9 times the risk (95% confidence interval [CI]: 1.7-4.9) of developing autism spectrum disorders compared to children born to mothers not exposed to valproate products during pregnancy. The absolute risks for autism spectrum disorders were 4.4% (95% CI: 2.6%-7.5%) in valproate-exposed children and 1.5% (95% CI: 1.5%-1.6%) in children not exposed to valproate products. Another observational study found that children who were exposed to valproate in utero had an increased risk of ADHD (adjusted HR 1.48; 95% CI, 1.09-2.00) compared with the unexposed children. Because these studies were observational in nature, conclusions regarding a causal association between in utero valproate exposure and an increased risk of autism spectrum disorder and ADHD cannot be considered definitive.

Other

There are published case reports of fatal hepatic failure in offspring of women who used valproate during pregnancy.

Animal

In developmental toxicity studies conducted in mice, rats, rabbits, and monkeys, increased rates of fetal structural abnormalities, intrauterine growth retardation, and embryo-fetal death occurred following administration of valproate to pregnant animals during organogenesis at clinically relevant doses (calculated on a body surface area [mg/m^2] basis). Valproate induced malformations of multiple organ systems, including skeletal, cardiac, and urogenital defects. In mice, in addition to other malformations, fetal neural tube defects have been reported following valproate administration during critical periods of organogenesis, and the teratogenic response correlated with peak maternal drug levels. Behavioral abnormalities (including cognitive, locomotor, and social interaction deficits) and brain histopathological changes have also been reported in mice and rat offspring exposed prenatally to clinically relevant doses of valproate.

8.2 Lactation

Risk Summary

Valproate is excreted in human milk. Data in the published literature describe the presence of valproate in human milk (range: 0.4 mcg/mL to 3.9 mcg/mL), corresponding to 1% to 10% of maternal serum levels. Valproate serum concentrations collected from breastfed infants aged 3 days postnatal to 12 weeks following delivery ranged from 0.7 mcg/mL to 4 mcg/mL, which were 1% to 6% of maternal serum valproate levels. A published study in children up to six years of age did not report adverse developmental or cognitive effects following exposure to valproate via breast milk [see Data (Human)].

There are no data to assess the effects of Depakote on milk production or excretion.

Clinical Considerations

The developmental and health benefits of breastfeeding should be considered along with the mother’s clinical need for Depakote and any potential adverse effects on the breastfed infant from Depakote or from the underlying maternal condition.

Monitor the breastfed infant for signs of liver damage including jaundice and unusual bruising or bleeding. There have been reports of hepatic failure and clotting abnormalities in offspring of women who used valproate during pregnancy [see Use in Specific Populations (8.1)].

Data

Human

In a published study, breast milk and maternal blood samples were obtained from 11 epilepsy patients taking valproate at doses ranging from 300 mg/day to 2,400 mg/day on postnatal days 3 to 6. In 4 patients who were taking valproate only, breast milk contained an average valproate concentration of 1.8 mcg/mL (range: 1.1 mcg/mL to 2.2 mcg/mL), which corresponded to 4.8% of the maternal plasma concentration (range: 2.7% to 7.4%). Across all patients (7 of whom were taking other AEDs concomitantly), similar results were obtained for breast milk concentration (1.8 mcg/mL, range: 0.4 mcg/mL to 3.9 mcg/mL) and maternal plasma ratio (5.1%, range: 1.3% to 9.6%).

A published study of 6 breastfeeding mother-infant pairs measured serum valproate levels during maternal treatment for bipolar disorder (750 mg/day or 1,000 mg/day). None of the mothers received valproate during pregnancy, and infants were aged from 4 weeks to 19 weeks at the time of evaluation. Infant serum levels ranged from 0.7 mcg/mL to 1.5 mcg/mL. With maternal serum valproate levels near or within the therapeutic range, infant exposure was 0.9% to 2.3% of maternal levels. Similarly, in 2 published case reports with maternal doses of 500 mg/day or 750 mg/day during breastfeeding of infants aged 3 months and 1 month, infant exposure was 1.5% and 6% that of the mother, respectively.

A prospective observational multicenter study evaluated the long-term neurodevelopmental effects of AED use on children. Pregnant women receiving monotherapy for epilepsy were enrolled with assessments of their children at ages 3 years and 6 years. Mothers continued AED therapy during the breastfeeding period. Adjusted IQs measured at 3 years for breastfed and non-breastfed children were 93 (n=11) and 90 (n=24), respectively. At 6 years, the scores for breastfed and non-breastfed children were 106 (n=11) and 94 (n=25), respectively (p=0.04). For other cognitive domains evaluated at 6 years, no adverse cognitive effects of continued exposure to an AED (including valproate) via breast milk were observed.

8.3 Females and Males of Reproductive Potential

Contraception

Women of childbearing potential should use effective contraception while taking valproate [see Boxed Warning, Warnings and Precautions (5.4), Drug Interactions (7), and Use in Specific Populations (8.1)]. This is especially important when valproate use is considered for a condition not usually associated with permanent injury or death such as prophylaxis of migraine headaches [see Contraindications (4)].

Infertility

There have been reports of male infertility coincident with valproate therapy [see Adverse Reactions (6.4)].

In animal studies, oral administration of valproate at clinically relevant doses resulted in adverse reproductive effects in males [see Nonclinical Toxicology (13.1)].

8.4 Pediatric Use

Experience has indicated that pediatric patients under the age of two years are at a considerably increased risk of developing fatal hepatotoxicity, especially those with the aforementioned conditions [see Boxed Warning and Warnings and Precautions (5.1)]. When Depakote ER is used in this patient group, it should be used with extreme caution and as a sole agent. The benefits of therapy should be weighed against the risks. Above the age of 2 years, experience in epilepsy has indicated that the incidence of fatal hepatotoxicity decreases considerably in progressively older patient groups.

Younger children, especially those receiving enzyme inducing drugs, will require larger maintenance doses to attain targeted total and unbound valproate concentrations. Pediatric patients (i.e., between 3 months and 10 years) have 50% higher clearances expressed on weight (i.e., mL/min/kg) than do adults. Over the age of 10 years, children have pharmacokinetic parameters that approximate those of adults.

The variability in free fraction limits the clinical usefulness of monitoring total serum valproic acid concentrations. Interpretation of valproic acid concentrations in children should include consideration of factors that affect hepatic metabolism and protein binding.

Pediatric Clinical Trials

Depakote was studied in seven pediatric clinical trials.

Two of the pediatric studies were double-blinded placebo-controlled trials to evaluate the efficacy of Depakote ER for the indications of mania (150 patients aged 10 to 17 years, 76 of whom were on Depakote ER) and migraine (304 patients aged 12 to 17 years, 231 of whom were on Depakote ER). Efficacy was not established for either the treatment of migraine or the treatment of mania. The most common drug-related adverse reactions (reported >5% and twice the rate of placebo) reported in the controlled pediatric mania study were nausea, upper abdominal pain, somnolence, increased ammonia, gastritis and rash.

The remaining five trials were long term safety studies. Two six-month pediatric studies were conducted to evaluate the long-term safety of Depakote ER for the indication of mania (292 patients aged 10 to 17 years). Two twelve-month pediatric studies were conducted to evaluate the long-term safety of Depakote ER for the indication of migraine (353 patients aged 12 to 17 years). One twelve-month study was conducted to evaluate the safety of Depakote Sprinkle Capsules in the indication of partial seizures (169 patients aged 3 to 10 years).

In these seven clinical trials, the safety and tolerability of Depakote in pediatric patients were shown to be comparable to those in adults [see Adverse Reactions (6)].

Juvenile Animal Toxicology

In studies of valproate in immature animals, toxic effects not observed in adult animals included retinal dysplasia in rats treated during the neonatal period (from postnatal day 4) and nephrotoxicity in rats treated during the neonatal and juvenile (from postnatal day 14) periods. The no-effect dose for these findings was less than the maximum recommended human dose on a mg/m^2 basis.

8.5 Geriatric Use

No patients above the age of 65 years were enrolled in double-blind prospective clinical trials of mania associated with bipolar illness. In a case review study of 583 patients, 72 patients (12%) were greater than 65 years of age. A higher percentage of patients above 65 years of age reported accidental injury, infection, pain, somnolence, and tremor. Discontinuation of valproate was occasionally associated with the latter two events. It is not clear whether these events indicate additional risk or whether they result from preexisting medical illness and concomitant medication use among these patients.

A study of elderly patients with dementia revealed drug related somnolence and discontinuation for somnolence [see Warnings and Precautions (5.16)]. The starting dose should be reduced in these patients, and dosage reductions or discontinuation should be considered in patients with excessive somnolence [see Dosage and Administration (2.5)].

There is insufficient information available to discern the safety and effectiveness of valproate for the prophylaxis of migraines in patients over 65.

The capacity of elderly patients (age range: 68 to 89 years) to eliminate valproate has been shown to be reduced compared to younger adults (age range: 22 to 26 years) [see Clinical Pharmacology (12.3)].

8.6 Effect of Disease

Liver Disease

Liver disease impairs the capacity to eliminate valproate [see Boxed Warning, Contraindications (4), Warnings and Precautions (5.1), and Clinical Pharmacology (12.3)].

10 OVERDOSAGE

Overdosage with valproate may result in somnolence, heart block, deep coma, and hypernatremia. Fatalities have been reported; however patients have recovered from valproate levels as high as 2,120 mcg/mL.

In overdose situations, the fraction of drug not bound to protein is high and hemodialysis or tandem hemodialysis plus hemoperfusion may result in significant removal of drug. The benefit of gastric lavage or emesis will vary with the time since ingestion. General supportive measures should be applied with particular attention to the maintenance of adequate urinary output.

Naloxone has been reported to reverse the CNS depressant effects of valproate overdosage. Because naloxone could theoretically also reverse the antiepileptic effects of valproate, it should be used with caution in patients with epilepsy.

11 DESCRIPTION

Divalproex sodium is a stable co-ordination compound comprised of sodium valproate and valproic acid in a 1:1 molar relationship and formed during the partial neutralization of valproic acid with 0.5 equivalent of sodium hydroxide. Chemically it is designated as sodium hydrogen bis(2-propylpentanoate). Divalproex sodium has the following structure:

Divalproex sodium occurs as a white powder with a characteristic odor.

Depakote ER 250 and 500 mg tablets are for oral administration. Depakote ER tablets contain divalproex sodium in a once-a-day extended-release formulation equivalent to 250 and 500 mg of valproic acid.

Inactive Ingredients

Depakote ER 250 and 500 mg tablets: FD&C Blue No. 1, hypromellose, lactose, microcrystalline cellulose, polyethylene glycol, potassium sorbate, propylene glycol, silicon dioxide, titanium dioxide, and triacetin.

In addition, 500 mg tablets contain iron oxide and polydextrose.

Meets USP Dissolution Test 2.

12 CLINICAL PHARMACOLOGY

12.1 Mechanism of Action

Divalproex sodium dissociates to the valproate ion in the gastrointestinal tract. The mechanisms by which valproate exerts its therapeutic effects have not been established. It has been suggested that its activity in epilepsy is related to increased brain concentrations of gamma-aminobutyric acid (GABA).

12.2 Pharmacodynamics

The relationship between plasma concentration and clinical response is not well documented. One contributing factor is the nonlinear, concentration dependent protein binding of valproate which affects the clearance of the drug. Thus, monitoring of total serum valproate may not provide a reliable index of the bioactive valproate species.

For example, because the plasma protein binding of valproate is concentration dependent, the free fraction increases from approximately 10% at 40 mcg/mL to 18.5% at 130 mcg/mL. Higher than expected free fractions occur in the elderly, in hyperlipidemic patients, and in patients with hepatic and renal diseases.

Epilepsy

The therapeutic range in epilepsy is commonly considered to be 50 to 100 mcg/mL of total valproate, although some patients may be controlled with lower or higher plasma concentrations.

Mania

In placebo-controlled clinical trials of acute mania, patients were dosed to clinical response with trough plasma concentrations between 85 and 125 mcg/mL [see Dosage and Administration (2.1)].

12.3 Pharmacokinetics

Absorption/Bioavailability

The absolute bioavailability of Depakote ER tablets administered as a single dose after a meal was approximately 90% relative to intravenous infusion.

When given in equal total daily doses, the bioavailability of Depakote ER is less than that of Depakote (divalproex sodium delayed-release tablets). In five multiple-dose studies in healthy subjects (N=82) and in subjects with epilepsy (N=86), when administered under fasting and nonfasting conditions, Depakote ER given once daily produced an average bioavailability of 89% relative to an equal total daily dose of Depakote given BID, TID, or QID. The median time to maximum plasma valproate concentrations (Cmax) after Depakote ER administration ranged from 4 to 17 hours. After multiple once-daily dosing of Depakote ER, the peak-to-trough fluctuation in plasma valproate concentrations was 10-20% lower than that of regular Depakote given BID, TID, or QID.

Conversion from Depakote to Depakote ER

When Depakote ER is given in doses 8 to 20% higher than the total daily dose of Depakote, the two formulations are bioequivalent. In two randomized, crossover studies, multiple daily doses of Depakote were compared to 8 to 20% higher once-daily doses of Depakote ER. In these two studies, Depakote ER and Depakote regimens were equivalent with respect to area under the curve (AUC; a measure of the extent of bioavailability). Additionally, valproate Cmax was lower, and Cmin was either higher or not different, for Depakote ER relative to Depakote regimens (see Table 8).

Table 8. Bioavailability of Depakote ER Tablets Relative to Depakote When Depakote ER Dose is 8 to 20% Higher
Study Population | Regimens | Relative Bioavailability
 | Depakote ER vs. Depakote | AUC24 | Cmax | Cmin
Healthy Volunteers (N=35) | 1,000 & 1,500 mg Depakote ER vs. 875 & 1,250 mg Depakote | 1.059 | 0.882 | 1.173
Patients with epilepsy on concomitant enzyme-inducing antiepilepsy drugs (N = 64) | 1,000 to 5,000 mg Depakote ER vs. 875 to 4,250 mg Depakote | 1.008 | 0.899 | 1.022

Concomitant antiepilepsy drugs (topiramate, phenobarbital, carbamazepine, phenytoin, and lamotrigine were evaluated) that induce the cytochrome P450 isozyme system did not significantly alter valproate bioavailability when converting between Depakote and Depakote ER.

Distribution

Protein Binding

The plasma protein binding of valproate is concentration dependent and the free fraction increases from approximately 10% at 40 mcg/mL to 18.5% at 130 mcg/mL. Protein binding of valproate is reduced in the elderly, in patients with chronic hepatic diseases, in patients with renal impairment, and in the presence of other drugs (e.g., aspirin). Conversely, valproate may displace certain protein-bound drugs (e.g., phenytoin, carbamazepine, warfarin, and tolbutamide) [see Drug Interactions (7.2) for more detailed information on the pharmacokinetic interactions of valproate with other drugs].

CNS Distribution

Valproate concentrations in cerebrospinal fluid (CSF) approximate unbound concentrations in plasma (about 10% of total concentration).

Metabolism

Valproate is metabolized almost entirely by the liver. In adult patients on monotherapy, 30-50% of an administered dose appears in urine as a glucuronide conjugate. Mitochondrial β-oxidation is the other major metabolic pathway, typically accounting for over 40% of the dose. Usually, less than 15-20% of the dose is eliminated by other oxidative mechanisms. Less than 3% of an administered dose is excreted unchanged in urine.

The relationship between dose and total valproate concentration is nonlinear; concentration does not increase proportionally with the dose, but rather, increases to a lesser extent due to saturable plasma protein binding. The kinetics of unbound drug are linear.

Elimination

Mean plasma clearance and volume of distribution for total valproate are 0.56 L/hr/1.73 m^2 and 11 L/1.73 m^2, respectively. Mean plasma clearance and volume of distribution for free valproate are 4.6 L/hr/1.73 m^2 and 92 L/1.73 m^2. Mean terminal half-life for valproate monotherapy ranged from 9 to 16 hours following oral dosing regimens of 250 to 1,000 mg.

The estimates cited apply primarily to patients who are not taking drugs that affect hepatic metabolizing enzyme systems. For example, patients taking enzyme-inducing antiepileptic drugs (carbamazepine, phenytoin, and phenobarbital) will clear valproate more rapidly. Because of these changes in valproate clearance, monitoring of antiepileptic concentrations should be intensified whenever concomitant antiepileptics are introduced or withdrawn.

Specific Populations

Effect of Age

Pediatric

The valproate pharmacokinetic profile following administration of Depakote ER was characterized in a multiple-dose, non-fasting, open label, multi-center study in children and adolescents. Depakote ER once daily doses ranged from 250-1,750 mg. Once daily administration of Depakote ER in pediatric patients (10-17 years) produced plasma VPA concentration-time profiles similar to those that have been observed in adults.

Elderly

The capacity of elderly patients (age range: 68 to 89 years) to eliminate valproate has been shown to be reduced compared to younger adults (age range: 22 to 26 years). Intrinsic clearance is reduced by 39%; the free fraction is increased by 44%. Accordingly, the initial dosage should be reduced in the elderly [see Dosage and Administration (2.4)].

Effect of Sex

There are no differences in the body surface area adjusted unbound clearance between males and females (4.8±0.17 and 4.7±0.07 L/hr per 1.73 m^2, respectively).

Effect of Race

The effects of race on the kinetics of valproate have not been studied.

Effect of Disease

Liver Disease

Liver disease impairs the capacity to eliminate valproate. In one study, the clearance of free valproate was decreased by 50% in 7 patients with cirrhosis and by 16% in 4 patients with acute hepatitis, compared with 6 healthy subjects. In that study, the half-life of valproate was increased from 12 to 18 hours. Liver disease is also associated with decreased albumin concentrations and larger unbound fractions (2 to 2.6 fold increase) of valproate. Accordingly, monitoring of total concentrations may be misleading since free concentrations may be substantially elevated in patients with hepatic disease whereas total concentrations may appear to be normal [see Boxed Warning, Contraindications (4), and Warnings and Precautions (5.1)].

Renal Disease

A slight reduction (27%) in the unbound clearance of valproate has been reported in patients with renal failure (creatinine clearance < 10 mL/minute); however, hemodialysis typically reduces valproate concentrations by about 20%. Therefore, no dosage adjustment appears to be necessary in patients with renal failure. Protein binding in these patients is substantially reduced; thus, monitoring total concentrations may be misleading.

Drug Interaction Studies with No Interaction or Likely Clinically Unimportant Interaction

Antacids

A study involving the co-administration of valproate 500 mg with commonly administered antacids (Maalox, Trisogel, and Titralac - 160 mEq doses) did not reveal any effect on the extent of absorption of valproate.

Chlorpromazine

A study involving the administration of 100 to 300 mg/day of chlorpromazine to schizophrenic patients already receiving valproate (200 mg BID) revealed a 15% increase in trough plasma levels of valproate.

Haloperidol

A study involving the administration of 6 to 10 mg/day of haloperidol to schizophrenic patients already receiving valproate (200 mg BID) revealed no significant changes in valproate trough plasma levels.

Cimetidine and Ranitidine

Cimetidine and ranitidine do not affect the clearance of valproate.

Acetaminophen

Valproate had no effect on any of the pharmacokinetic parameters of acetaminophen when it was concurrently administered to three epileptic patients.

Clozapine

In psychotic patients (n=11), no interaction was observed when valproate was co-administered with clozapine.

Lithium

Co-administration of valproate (500 mg BID) and lithium carbonate (300 mg TID) to normal male volunteers (n=16) had no effect on the steady-state kinetics of lithium.

Lorazepam

Concomitant administration of valproate (500 mg BID) and lorazepam (1 mg BID) in normal male volunteers (n=9) was accompanied by a 17% decrease in the plasma clearance of lorazepam.

Olanzapine

No dose adjustment for olanzapine is necessary when olanzapine is administered concomitantly with valproate. Co-administration of valproate (500 mg BID) and olanzapine (5 mg) to healthy adults (n=10) caused 15% reduction in Cmax and 35% reduction in AUC of olanzapine.

Oral Contraceptive Steroids

Administration of a single-dose of ethinyloestradiol (50 mcg)/levonorgestrel (250 mcg) to 6 women on valproate (200 mg BID) therapy for 2 months did not reveal any pharmacokinetic interaction.

13 NONCLINICAL TOXICOLOGY

13.1 Carcinogenesis, Mutagenesis, and Impairment of Fertility

Carcinogenesis

Valproate was administered orally to rats and mice at doses of 80 and 170 mg/kg/day (less than the maximum recommended human dose on a mg/m^2 basis) for two years. The primary findings were an increase in the incidence of subcutaneous fibrosarcomas in high-dose male rats receiving valproate and a dose-related trend for benign pulmonary adenomas in male mice receiving valproate.

Mutagenesis

Valproate was not mutagenic in an in vitro bacterial assay (Ames test), did not produce dominant lethal effects in mice, and did not increase chromosome aberration frequency in an in vivo cytogenetic study in rats. Increased frequencies of sister chromatid exchange (SCE) have been reported in a study of epileptic children taking valproate; this association was not observed in another study conducted in adults.

Impairment of Fertility

In chronic toxicity studies in juvenile and adult rats and dogs, administration of valproate resulted in testicular atrophy and reduced spermatogenesis at oral doses of 400 mg/kg/day or greater in rats (approximately equal to or greater than the maximum recommended human dose (MRHD) on a mg/m^2 basis) and 150 mg/kg/day or greater in dogs (approximately equal to or greater than the MRHD on a mg/m^2 basis). Fertility studies in rats have shown no effect on fertility at oral doses of valproate up to 350 mg/kg/day (approximately equal to the MRHD on a mg/m^2 basis) for 60 days.

14 CLINICAL STUDIES

14.1 Mania

The effectiveness of Depakote ER for the treatment of acute mania is based in part on studies establishing the effectiveness of Depakote (divalproex sodium delayed release tablets) for this indication. Depakote ER’s effectiveness was confirmed in one randomized, double-blind, placebo-controlled, parallel group, 3-week, multicenter study. The study was designed to evaluate the safety and efficacy of Depakote ER in the treatment of bipolar I disorder, manic or mixed type, in adults. Adult male and female patients who had a current DSM-IV TR primary diagnosis of bipolar I disorder, manic or mixed type, and who were hospitalized for acute mania, were enrolled into this study. Depakote ER was initiated at a dose of 25 mg/kg/day given once daily, increased by 500 mg/day on Day 3, then adjusted to achieve plasma valproate concentrations in the range of 85-125 mcg/mL. Mean daily Depakote ER doses for observed cases were 2,362 mg (range: 500-4,000), 2,874 mg (range: 1,500-4,500), 2,993 mg (range: 1,500-4,500), 3,181 mg (range: 1,500-5,000), and 3,353 mg (range: 1,500-5,500) at Days 1, 5, 10, 15, and 21, respectively. Mean valproate concentrations were 96.5 mcg/mL, 102.1 mcg/mL, 98.5 mcg/mL, 89.5 mcg/mL at Days 5, 10, 15 and 21, respectively. Patients were assessed on the Mania Rating Scale (MRS; score ranges from 0-52).

Depakote ER was significantly more effective than placebo in reduction of the MRS total score.

14.2 Epilepsy

The efficacy of valproate in reducing the incidence of complex partial seizures (CPS) that occur in isolation or in association with other seizure types was established in two controlled trials.

In one, multi-clinic, placebo controlled study employing an add-on design (adjunctive therapy), 144 patients who continued to suffer eight or more CPS per 8 weeks during an 8 week period of monotherapy with doses of either carbamazepine or phenytoin sufficient to assure plasma concentrations within the "therapeutic range" were randomized to receive, in addition to their original antiepilepsy drug (AED), either Depakote or placebo. Randomized patients were to be followed for a total of 16 weeks. The following table presents the findings.

Table 9. Adjunctive Therapy Study Median Incidence of CPS per 8 Weeks
Add-on Treatment | Number of Patients | Baseline Incidence | Experimental Incidence
Depakote | 75 | 16.0 | 8.9*
Placebo | 69 | 14.5 | 11.5
* Reduction from baseline statistically significantly greater for valproate than placebo at p ≤ 0.05 level.

Figure 1 presents the proportion of patients (X axis) whose percentage reduction from baseline in complex partial seizure rates was at least as great as that indicated on the Y axis in the adjunctive therapy study. A positive percent reduction indicates an improvement (i.e., a decrease in seizure frequency), while a negative percent reduction indicates worsening. Thus, in a display of this type, the curve for an effective treatment is shifted to the left of the curve for placebo. This figure shows that the proportion of patients achieving any particular level of improvement was consistently higher for valproate than for placebo. For example, 45% of patients treated with valproate had a ≥ 50% reduction in complex partial seizure rate compared to 23% of patients treated with placebo.

Figure 1

The second study assessed the capacity of valproate to reduce the incidence of CPS when administered as the sole AED. The study compared the incidence of CPS among patients randomized to either a high or low dose treatment arm. Patients qualified for entry into the randomized comparison phase of this study only if 1) they continued to experience 2 or more CPS per 4 weeks during an 8 to 12 week long period of monotherapy with adequate doses of an AED (i.e., phenytoin, carbamazepine, phenobarbital, or primidone) and 2) they made a successful transition over a two week interval to valproate. Patients entering the randomized phase were then brought to their assigned target dose, gradually tapered off their concomitant AED and followed for an interval as long as 22 weeks. Less than 50% of the patients randomized, however, completed the study. In patients converted to Depakote monotherapy, the mean total valproate concentrations during monotherapy were 71 and 123 mcg/mL in the low dose and high dose groups, respectively.

The following table presents the findings for all patients randomized who had at least one post-randomization assessment.

Table 10. Monotherapy Study Median Incidence of CPS per 8 Weeks
Treatment | Number of Patients | Baseline Incidence | Randomized Phase Incidence
High dose Valproate | 131 | 13.2 | 10.7*
Low dose Valproate | 134 | 14.2 | 13.8
* Reduction from baseline statistically significantly greater for high dose than low dose at p ≤ 0.05 level.

Figure 2 presents the proportion of patients (X axis) whose percentage reduction from baseline in complex partial seizure rates was at least as great as that indicated on the Y axis in the monotherapy study. A positive percent reduction indicates an improvement (i.e., a decrease in seizure frequency), while a negative percent reduction indicates worsening. Thus, in a display of this type, the curve for a more effective treatment is shifted to the left of the curve for a less effective treatment. This figure shows that the proportion of patients achieving any particular level of reduction was consistently higher for high dose valproate than for low dose valproate. For example, when switching from carbamazepine, phenytoin, phenobarbital or primidone monotherapy to high dose valproate monotherapy, 63% of patients experienced no change or a reduction in complex partial seizure rates compared to 54% of patients receiving low dose valproate.

Figure 2

Information on pediatric studies is presented in section 8.

14.3 Migraine

The results of a multicenter, randomized, double-blind, placebo-controlled, parallel-group clinical trial demonstrated the effectiveness of Depakote ER in the prophylactic treatment of migraine headache. This trial recruited patients with a history of migraine headaches with or without aura occurring on average twice or more a month for the preceding three months. Patients with cluster or chronic daily headaches were excluded. Women of childbearing potential were allowed in the trial if they were deemed to be practicing an effective method of contraception.

Patients who experienced ≥ 2 migraine headaches in the 4-week baseline period were randomized in a 1:1 ratio to Depakote ER or placebo and treated for 12 weeks. Patients initiated treatment on 500 mg once daily for one week, and were then increased to 1,000 mg once daily with an option to permanently decrease the dose back to 500 mg once daily during the second week of treatment if intolerance occurred. Ninety-eight of 114 Depakote ER-treated patients (86%) and 100 of 110 placebo-treated patients (91%) treated at least two weeks maintained the 1,000 mg once daily dose for the duration of their treatment periods. Treatment outcome was assessed on the basis of reduction in 4-week migraine headache rate in the treatment period compared to the baseline period.

Patients (50 male, 187 female) ranging in age from 16 to 69 were treated with Depakote ER (N=122) or placebo (N=115). Four patients were below the age of 18 and 3 were above the age of 65. Two hundred and two patients (101 in each treatment group) completed the treatment period. The mean reduction in 4-week migraine headache rate was 1.2 from a baseline mean of 4.4 in the Depakote ER group, versus 0.6 from a baseline mean of 4.2 in the placebo group. The treatment difference was statistically significant (see Figure 3).

Figure 3 Mean Reduction In 4-Week Migraine Headache Rates

15 REFERENCES

1. Meador KJ, Baker GA, Browning N, et al. Fetal antiepileptic drug exposure and cognitive outcomes at age 6 years (NEAD study): a prospective observational study. Lancet Neurology 2013; 12 (3):244-252.

16 HOW SUPPLIED/STORAGE AND HANDLING

Depakote ER 250 mg is available as white ovaloid tablets containing divalproex sodium equivalent to 250 mg of valproic acid in each tablet in the following package sizes:

- Bottles of 100, tablets with the “a” logo and the code HF – NDC 0074-3826-13
- Bottles of 100, tablets with the code HF – NDC 0074-7401-13

Depakote ER 500 mg is available as gray ovaloid tablets containing divalproex sodium equivalent to 500 mg of valproic acid in each tablet in the following packaging sizes:

- Bottles of 100, tablets with the “a” logo and the code HC – NDC 0074-7126-13
- Bottles of 100, tablets with the code HC – NDC 0074-7402-13
- Bottles of 500, tablets with the “a” logo and the code HC – NDC 0074-7126-53
- Unit Dose Packages of 100, tablets with the “a” logo and the code HC – NDC 0074-7126-11

Recommended Storage: Store tablets at 25°C (77°F); excursions permitted to 15-30°C (59-86°F) [see USP Controlled Room Temperature].

17 PATIENT COUNSELING INFORMATION

Advise the patient to read the FDA-approved patient labeling (Medication Guide).

Hepatotoxicity

Warn patients and guardians that nausea, vomiting, abdominal pain, anorexia, diarrhea, asthenia, and/or jaundice can be symptoms of hepatotoxicity and, therefore, require further medical evaluation promptly [see Warnings and Precautions (5.1)].

Pancreatitis

Warn patients and guardians that abdominal pain, nausea, vomiting, and/or anorexia can be symptoms of pancreatitis and, therefore, require further medical evaluation promptly [see Warnings and Precautions (5.5)].

Birth Defects and Decreased IQ

Inform pregnant women and women of childbearing potential (including girls beginning the onset of puberty) that use of valproate during pregnancy increases the risk of birth defects, decreased IQ, and neurodevelopmental disorders in children who were exposed in utero. Advise women to use effective contraception while taking valproate. When appropriate, counsel these patients about alternative therapeutic options. This is particularly important when valproate use is considered for a condition not usually associated with permanent injury or death such as prophylaxis of migraine headache [see Contraindications (4)]. Advise patients to read the Medication Guide, which appears as the last section of the labeling [see Warnings and Precautions (5.2, 5.3, 5.4) and Use in Specific Populations (8.1)].

Pregnancy Registry

Advise women of childbearing potential to discuss pregnancy planning with their doctor and to contact their doctor immediately if they think they are pregnant.

Encourage women who are taking Depakote ER to enroll in the North American Antiepileptic Drug (NAAED) Pregnancy Registry if they become pregnant. This registry is collecting information about the safety of antiepileptic drugs during pregnancy. To enroll, patients can call the toll free number 1-888-233-2334 or visit the website, http://www.aedpregnancyregistry.org/ [see Use in Specific Populations (8.1)].

Suicidal Thinking and Behavior

Counsel patients, their caregivers, and families that AEDs, including Depakote ER, may increase the risk of suicidal thoughts and behavior and to be alert for the emergence or worsening of symptoms of depression, any unusual changes in mood or behavior, or the emergence of suicidal thoughts, behavior, or thoughts about self-harm. Instruct patients, caregivers, and families to report behaviors of concern immediately to the healthcare providers [see Warnings and Precautions (5.7)].

Hyperammonemia

Inform patients of the signs and symptoms associated with hyperammonemic encephalopathy and to notify the prescriber if any of these symptoms occur [see Warnings and Precautions (5.9, 5.10)].

CNS Depression

Since valproate products may produce CNS depression, especially when combined with another CNS depressant (e.g., alcohol), advise patients not to engage in hazardous activities, such as driving an automobile or operating dangerous machinery, until it is known that they do not become drowsy from the drug.

Drug Reaction with Eosinophilia and Systemic Symptoms (DRESS)/Multiorgan Hypersensitivity Reactions

Instruct patients that a fever associated with other organ system involvement (rash, lymphadenopathy, etc.) may be drug-related. Advise patients to report such reactions to a healthcare provider immediately [see Warnings and Precautions (5.12)].

Serious Dermatologic Reactions

Advise patients of the early signs and symptoms of severe cutaneous adverse reactions and to report any occurrence immediately to a healthcare provider [see Warnings and Precautions (5.13)].

Angioedema

Advise patients to discontinue Depakote and seek immediate medical care if they develop signs or symptoms of angioedema, such as facial, perioral, or upper airway swelling [see Warnings and Precautions (5.14)].

Medication Residue in the Stool

Instruct patients to notify their healthcare provider if they notice a medication residue in the stool [see Warnings and Precautions (5.20)].

250 mg is Mfd. by AbbVie LTD, Barceloneta, PR 00617

500 mg is Mfd. by AbbVie Inc., North Chicago, IL 60064 U.S.A. or

AbbVie LTD, Barceloneta, PR 00617

For AbbVie Inc., North Chicago, IL 60064 U.S.A.

©2000-2025 AbbVie Inc.

20091021 R2

MEDICATION GUIDE
DEPAKOTE ER (dep-a-kOte)
(divalproex sodium)
Extended-Release Tablets, for oral use
DEPAKOTE (dep-a-kOte)
(divalproex sodium)
Delayed-Release Tablets, for oral use
DEPAKOTE Sprinkle Capsules (dep-a-kOte)
(divalproex sodium delayed release capsules)
for oral use

What is the most important information I should know about DEPAKOTE?
Do not stop Depakote without first talking to a healthcare provider. Stopping Depakote suddenly can cause serious problems. Stopping a seizure medicine suddenly in a patient who has epilepsy can cause seizures that will not stop (status epilepticus).
Depakote can cause serious side effects, including:
1. Serious liver damage that can cause death, especially in children younger than 2 years old and patients with mitochondrial disorders. The risk of getting this serious liver damage is more likely to happen within the first 6 months of treatment.
Call your healthcare provider right away if you get any of the following symptoms:

- feeling very weak, tired, or uncomfortable (malaise)
- swelling of your face
- not feeling hungry
- nausea or vomiting that does not go away
- diarrhea
- pain on the right side of your stomach (abdomen)
- dark urine
- yellowing of your skin or the whites of your eyes
- loss of seizure control in people with epilepsy

In some cases, liver damage may continue even though the medicine is stopped. Your healthcare provider will do blood tests to check your liver before and during treatment with DEPAKOTE.
2. Depakote may harm your unborn baby.

- If you take Depakote during pregnancy for any medical condition, your baby is at risk for serious birth defects that affect the brain and spinal cord (such as spina bifida or neural tube defects). These defects can begin in the first month, even before you know you are pregnant. Other birth defects that affect the structures of the heart, head, arms, legs, and the opening where the urine comes out (urethra) on the bottom of the penis can also happen. Decreased hearing or hearing loss can also happen.
- Birth defects may occur even in children born to women who are not taking any medicines and do not have other risk factors.
- Taking folic acid supplements before getting pregnant and during early pregnancy can lower the chance of having a baby with a neural tube defect.
- If you take Depakote during pregnancy for any medical condition, your child is at risk for having lower IQ and may be at risk for developing autism or attention deficit/hyperactivity disorder.
- There may be other medicines to treat your condition that have a lower chance of causing birth defects, decreased IQ, or other disorders in your child.
- Women who are pregnant must not take Depakote to prevent migraine headaches.
- All women of childbearing age (including girls from the start of puberty) should talk to their healthcare provider about using other possible treatments instead of Depakote. If the decision is made to use Depakote, you should use effective birth control (contraception).
- Tell your healthcare provider right away if you become pregnant while taking Depakote. You and your healthcare provider should decide if you will continue to take Depakote while you are pregnant.
- Pregnancy Registry: If you become pregnant while taking Depakote, talk to your healthcare provider about registering with the North American Antiepileptic Drug (NAAED) Pregnancy Registry. You can enroll in this registry by calling toll-free 1-888-233-2334 or by visiting the website, http://www.aedpregnancyregistry.org/. The purpose of this registry is to collect information about the safety of antiepileptic drugs during pregnancy.

3. Swelling (Inflammation) and bleeding (hemorrhaging) of your pancreas that can cause death.
Call your healthcare provider right away if you have any of these symptoms:

- severe stomach pain that you may also feel in your back
- nausea or vomiting that does not go away
- not feeling hungry

4. Like other antiepileptic drugs, Depakote may cause suicidal thoughts or actions in a very small number of people, about 1 in 500.
Call a healthcare provider right away if you have any of these symptoms, especially if they are new, worse, or worry you:

- thoughts about suicide or dying
- suicide attempt
- new or worse depression
- new or worse anxiety
- feeling agitated or restless
- panic attacks
- trouble sleeping (insomnia)
- new or worse irritability
- acting aggressive, being angry, or violent
- acting on dangerous impulses
- an extreme increase in activity and talking (mania)
- other unusual changes in behavior or mood

How can I watch for early symptoms of suicidal thoughts and actions?

- Pay attention to any changes, especially sudden changes in mood, behaviors, thoughts, or feelings.
- Keep all follow-up visits with your healthcare provider as scheduled.

Call your healthcare provider between visits as needed, especially if you are worried about symptoms.
Suicidal thoughts or actions can be caused by things other than medicines. If you have suicidal thoughts or actions, your healthcare provider may check for other causes.

What is Depakote?
Depakote ER tablets, Depakote delayed-release tablets, and Depakote Sprinkle Capsules are prescription medicines used:

- alone or with other medicines to treat:
  ○ complex partial seizures in adults and children 10 years of age and older
  ○ simple and complex absence seizures
- with other medications to treat:
  ○ patients with multiple seizure types that include absence seizures

Depakote ER tablets and Depakote delayed-release tablets are also used to prevent migraine headaches.
Depakote ER tablets are also used to treat acute manic or mixed episodes associated with bipolar disorder with or without psychotic features.
Depakote delayed-release tablets are also used to treat manic episodes associated with bipolar disorder.

Do not take Depakote if you:

- have liver problems.
- have or think you have a genetic liver problem caused by a mitochondrial disorder such as Alpers-Huttenlocher syndrome.
- are allergic to divalproex sodium, valproic acid, sodium valproate, or any of the ingredients in Depakote. See the end of this Medication Guide for a complete list of ingredients in Depakote.
- have a genetic problem called a urea cycle disorder.
- are taking it to prevent migraine headaches and are either pregnant or may become pregnant because you are not using effective birth control (contraception).

Before taking Depakote, tell your healthcare provider about all of your medical conditions including if you:

- have or have had liver problems.
- have or think you have a genetic liver problem caused by a mitochondrial disorder such as Alpers-Huttenlocher syndrome.
- drink alcohol.
- have or have had depression, suicidal thoughts or behavior, unusual changes in mood, or thoughts about self-harm.
- are male and plan to father a child. DEPAKOTE may cause fertility problems, which may affect your ability to father a child. Talk to your healthcare provider if this is a problem for you.
- are pregnant or may become pregnant. DEPAKOTE may harm your unborn baby. See “2. Depakote may harm your unborn baby” above for more information.
- are breastfeeding. Depakote can pass into breast milk and may harm your baby. Talk to your healthcare provider about the best way to feed your baby if you take Depakote.

Tell your healthcare provider about all the medicines you take, including prescription and over-the-counter medicines, vitamins, and herbal supplements.
DEPAKOTE may affect the way other medicines work, and other medicines may affect how DEPAKOTE works. Using DEPAKOTE with other medicines can cause serious side effects. Do not start or stop other medicines without talking to your healthcare provider.
Especially tell your healthcare provider if you take:

- medicines that can affect how the liver breaks down other medicines (such as phenytoin, carbamazepine, felbamate, phenobarbital, primidone, rifampin)
- aspirin, carbapenem antibiotics, or estrogen-containing hormonal contraceptives
- methotrexate
- topiramate
- cannabidiol

You can ask your healthcare provider or pharmacist for a list of these medicines if you are not sure.
Know the medicines you take. Keep a list of them and show it to your healthcare provider and pharmacist each time you get a new medicine.

How should I take Depakote?

- Depakote comes in different dosage forms.
- Take Depakote exactly as your healthcare provider tells you. Your healthcare provider will tell you how much Depakote to take and when to take it.
- Your healthcare provider may change your dose, if needed.
- Do not change your dose of Depakote without talking to your healthcare provider.
- Do not stop taking Depakote without first talking to your healthcare provider. Stopping Depakote suddenly can cause serious problems. See “What is the most important information I should know about Depakote?”.
- Swallow Depakote ER tablets or DEPAKOTE delayed-release tablets whole. Do not crush or chew them. Tell your healthcare provider if you cannot swallow Depakote ER tablets or DEPAKOTE delayed-release tablets whole. You may need a different medicine.
- Depakote Sprinkle Capsules may be swallowed whole, or the capsule may be opened and the contents may be mixed into a small amount of soft food, such as applesauce or pudding. See the Instructions for Use that comes with this Medication Guide for detailed instructions on how to use Depakote Sprinkle Capsules.
- If you miss a dose of DEPAKOTE ER tablets or DEPAKOTE delayed-release tablets, take it as soon as you remember unless it’s almost time for your next dose. Take the next dose at your regular time. Do not take 2 doses at the same time.
- If you take too much DEPAKOTE, call your healthcare provider or poison control center right away.

What should I avoid while taking Depakote?

- Do not drink alcohol while taking Depakote. Depakote and alcohol can affect each other causing side effects such as sleepiness and dizziness.
- Do not drive a car, operate dangerous machinery, or do dangerous activities until you know how Depakote affects you. Depakote can slow your thinking and motor skills and may affect your vision.

What are the possible side effects of Depakote?
Call your healthcare provider right away if you have any of the symptoms listed below. Your healthcare provider may do additional tests before and during your treatment with DEPAKOTE. Your healthcare provider may reduce your dose, temporarily stop, or permanently stop treatment if you have certain side effects.
Depakote can cause serious side effects including:

- See “What is the most important information I should know about Depakote?”
- bleeding problems. Call your healthcare provider if you have any symptoms of bleeding, including:

- bruising or red or purple spots on your skin

- vomiting blood or vomit that looks like coffee grounds

- bleeding from your mouth or nose

- blood in your stools or black stools (looks like tar)

- cough up blood or blood clots

- pain and swelling in your joints

- increased ammonia levels in your blood. High ammonia levels can seriously affect your mental activities, slow your alertness, make you feel tired, or cause vomiting (encephalopathy). This has happened when DEPAKOTE is taken alone or with a medicine called topiramate. Call your health care provider if you have any of these symptoms.
- low body temperature (hypothermia). A drop in your body temperature to less than 95°F can happen during treatment with DEPAKOTE. Call your healthcare provider if you have any of the following symptoms:

- feeling tired

- drowsiness

- confusion

- coma

- memory loss

- shivering

- severe multiorgan or skin reactions. Treatment with DEPAKOTE may cause serious or life-threatening allergic reactions that may affect your skin or other parts of your body. Stop taking DEPAKOTE, and contact your healthcare provider or get medical help right away, if you develop any of these symptoms:

- skin rash

- swelling of your lymph nodes

- hives

- swelling of your face, eyes, lips, tongue, or throat

- blistering and peeling of your skin

- trouble swallowing or breathing

- sores in your mouth

- drowsiness or sleepiness in the elderly. This extreme drowsiness may cause you to eat or drink less than you normally would. Tell your healthcare provider if you are not able to eat or drink as you normally do. Your healthcare provider may start you at a lower dose of Depakote.
- medicine residue in your stool. Tell your healthcare provider if you have or think you may have medicine residue in your stool.

The common side effects of DEPAKOTE include:

- headache

- low blood platelet count

- weakness

- stomach burning, fullness, or bloating after eating

- sleepiness

- nausea

- dizziness

- vomiting

- tremors

- stomach pain

- difficulty falling or staying asleep

- diarrhea

- double vision

- infection

- hair loss (alopecia)

These are not all of the possible side effects of Depakote.
Call your doctor for medical advice about side effects. You may report side effects to FDA at 1-800-FDA-1088.

How should I store Depakote?

- Store Depakote ER Tablets at room temperature between 68°F to 77°F (20°C to 25°C).
- Store Depakote delayed release tablets below 86°F (30°C).
- Store Depakote Sprinkle Capsules below 77°F (25°C).

Keep Depakote and all medicines out of the reach of children.

General information about the safe and effective use of Depakote
Medicines are sometimes prescribed for purposes other than those listed in a Medication Guide. Do not use Depakote for a condition for which it was not prescribed. Do not give Depakote to other people, even if they have the same symptoms that you have. It may harm them.
You can ask your pharmacist or healthcare provider for information about Depakote that is written for health professionals.

What are the ingredients in Depakote?
Active ingredient: divalproex sodium
Inactive ingredients:

- Depakote ER tablets: FD&C Blue No. 1, hypromellose, lactose, microcrystalline cellulose, polyethylene glycol, potassium sorbate, propylene glycol, silicon dioxide, titanium dioxide, and triacetin. The 500 mg tablets also contain iron oxide and polydextrose.
- Depakote delayed-release tablets: cellulosic polymers, diacetylated monoglycerides, povidone, pregelatinized starch (contains corn starch), silica gel, talc, titanium dioxide, and vanillin.
  - Individual tablets also contain:
    125 mg tablets: FD&C Blue No. 1 and FD&C Red No. 40,
    250 mg tablets: FD&C Yellow No. 6 and iron oxide,
    500 mg tablets: D&C Red No. 30, FD&C Blue No. 2, and iron oxide.
- Depakote Sprinkle Capsules: cellulosic polymers, D&C Red No. 28, FD&C Blue No. 1 gelatin, iron oxide, magnesium stearate, silica gel, titanium dioxide, and triethyl citrate.

Manufactured by:
Depakote ER tablets:
250 mg is Mfd. by AbbVie LTD, Barceloneta, PR 00617
500 mg is Mfd. by AbbVie Inc., North Chicago, IL 60064 U.S.A. or
AbbVie LTD, Barceloneta, PR 00617
For AbbVie Inc., North Chicago, IL 60064 U.S.A.
Depakote delayed-release tablets:
Mfd. by AbbVie LTD, Barceloneta, PR 00617
For AbbVie Inc., North Chicago, IL 60064, U.S.A.
Depakote Sprinkle Capsules:
AbbVie Inc., North Chicago, IL 60064, U.S.A.
For more information, go to www.rxabbvie.com or call 1-800-633-9110.

This Medication Guide has been approved by the U.S. Food and Drug Administration. Revised: May 2025

©1983-2025 AbbVie Inc.

20091021 R2

PACKAGE LABEL

NDC 0074-3826-13

100 Tablets

Once-Daily Dosing

DEPAKOTE® ER

DIVALPROEX SODIUM EXTENDED-RELEASE TABLETS

250 mg Valproic Acid Activity

Dispense the accompanying Medication Guide to each patient.

Rx only abbvie

PACKAGE LABEL

NDC 0074-7401-13

100 Tablets

Once-Daily Dosing

DEPAKOTE® ER

DIVALPROEX SODIUM EXTENDED-RELEASE TABLETS

250 mg Valproic Acid Activity

Dispense the accompanying Medication Guide to each patient.

Rx only abbvie

PACKAGE LABEL

NDC 0074-7126-11

100 Tablets

TO OPEN

Tear Back Along Perforation

Dispense the accompanying Medication Guide to each patient.

Rx only

Once-Daily Dosing

DEPAKOTE® ER

DIVALPROEX SODIUM EXTENDED-RELEASE TABLETS

500 mg Valproic Acid Activity

Tamper-Evident: Do not accept if opened or seal has been broken.

THIS PACKAGE FOR HOUSEHOLDS WITHOUT YOUNG CHILDREN

PACKAGE LABEL

NDC 0074-7126-13

100 Tablets

Once-Daily Dosing

DEPAKOTE® ER

DIVALPROEX SODIUM EXTENDED-RELEASE TABLETS

500 mg Valproic Acid Activity

Dispense the accompanying Medication Guide to each patient.

Rx only abbvie

PACKAGE LABEL

NDC 0074-7402-13

100 Tablets

Once-Daily Dosing

DEPAKOTE® ER

DIVALPROEX SODIUM EXTENDED-RELEASE TABLETS

500 mg Valproic Acid Activity

Dispense the accompanying Medication Guide to each patient.

Rx only abbvie